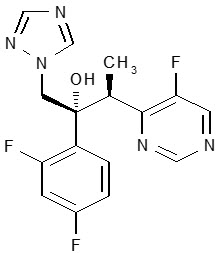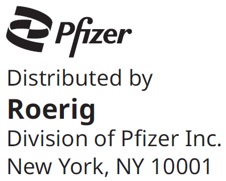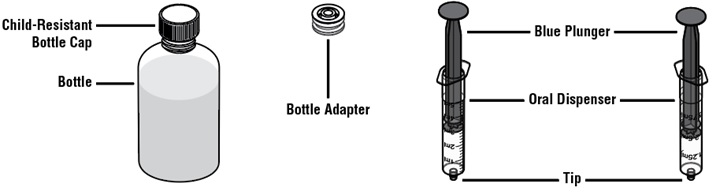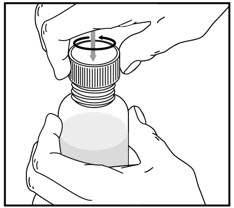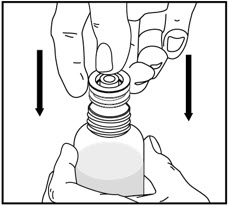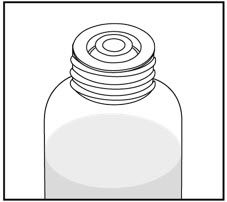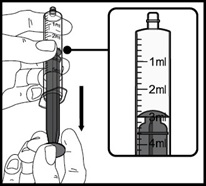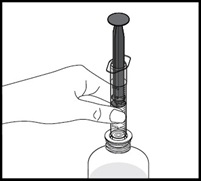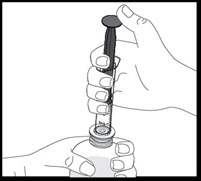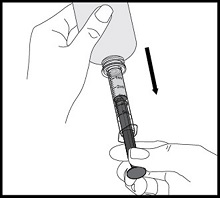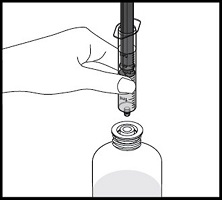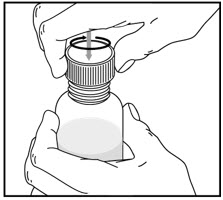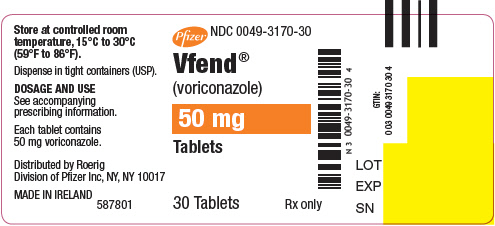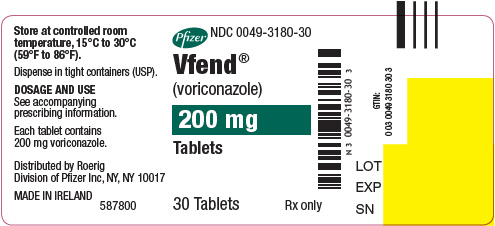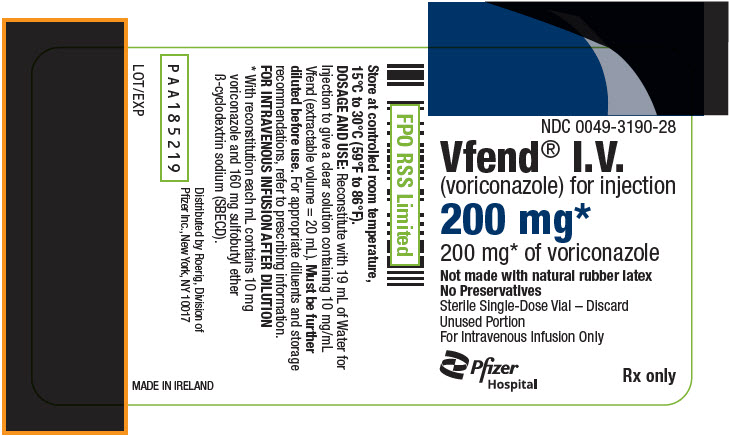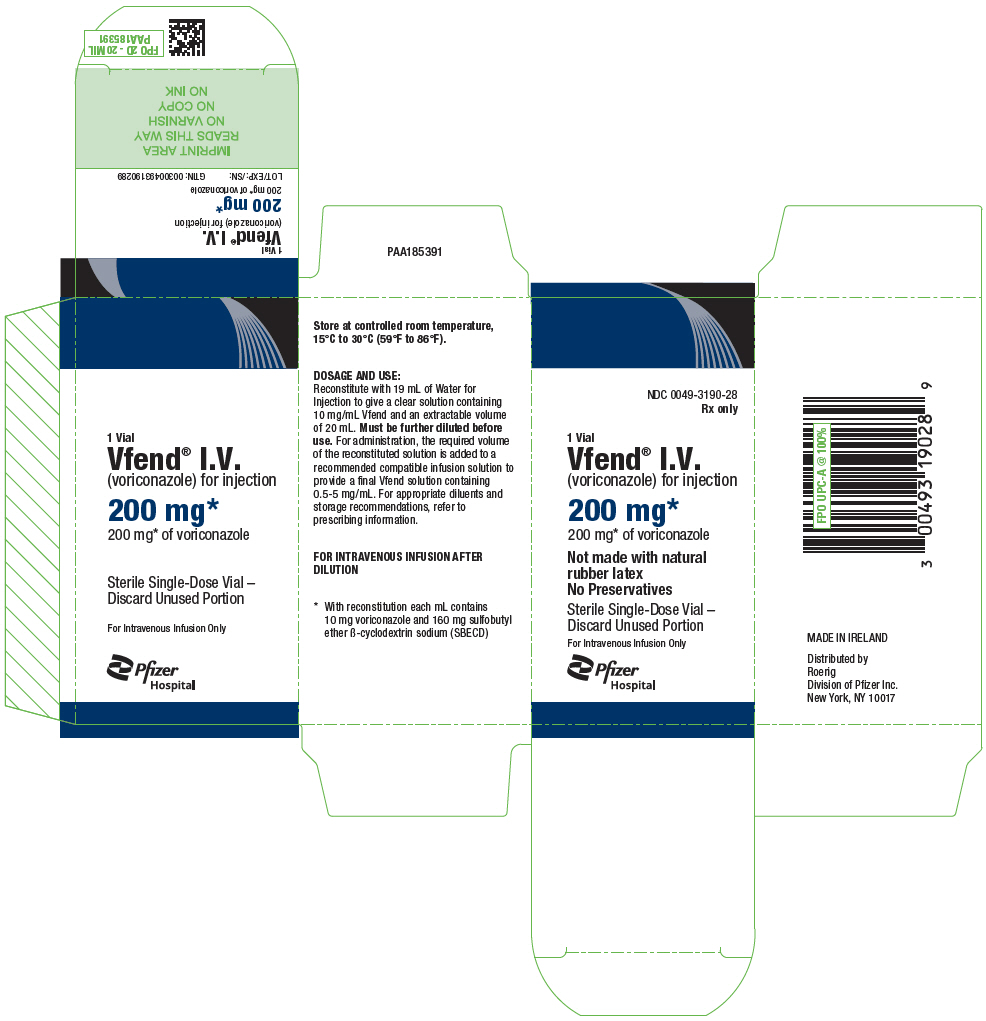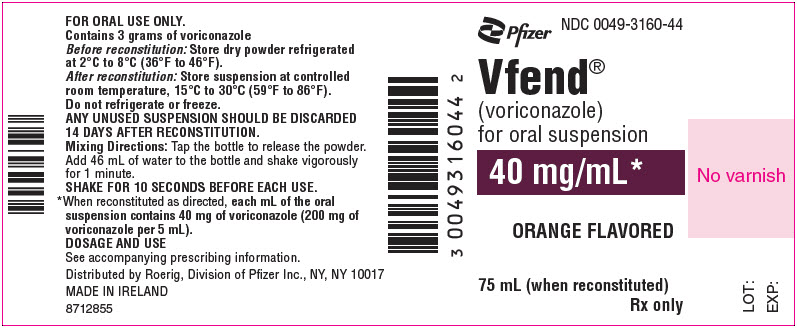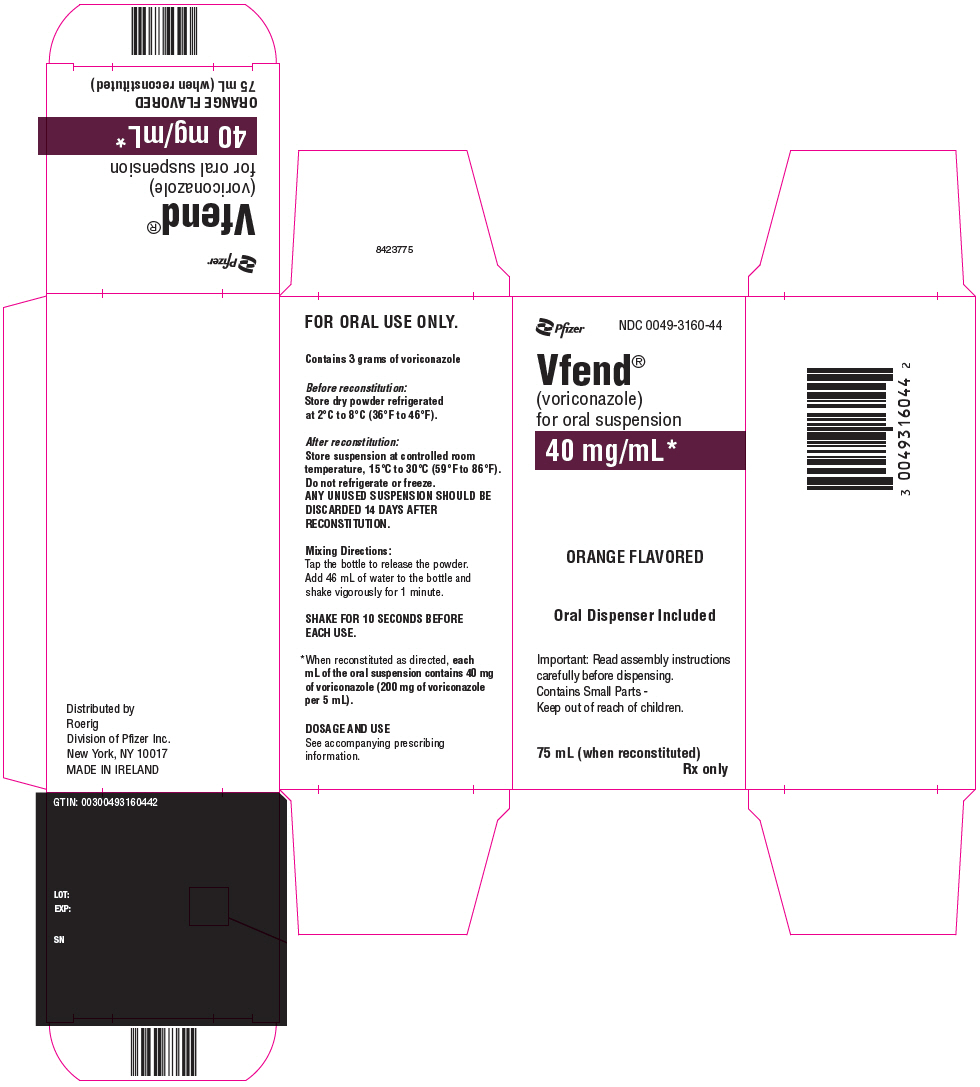 DRUG LABEL: VFEND
NDC: 0049-3170 | Form: TABLET, FILM COATED
Manufacturer: Roerig
Category: prescription | Type: HUMAN PRESCRIPTION DRUG LABEL
Date: 20260226

ACTIVE INGREDIENTS: VORICONAZOLE 50 mg/1 1
INACTIVE INGREDIENTS: LACTOSE MONOHYDRATE; CROSCARMELLOSE SODIUM; POVIDONE, UNSPECIFIED; MAGNESIUM STEARATE; HYPROMELLOSE, UNSPECIFIED; TITANIUM DIOXIDE; TRIACETIN

HIGHLIGHTS OF PRESCRIBING INFORMATION

These highlights do not include all the information needed to use VFEND safely and effectively. See full prescribing information for VFEND.
VFEND® (voriconazole) tablets, for oral use
VFEND® (voriconazole) for oral suspension
VFEND® (voriconazole) for injection, for intravenous use
Initial U.S. Approval: 2002

RECENT MAJOR CHANGES

Contraindications (4) | 1/2026

1 INDICATIONS AND USAGE

VFEND is an azole antifungal indicated for the treatment of adults and pediatric patients 2 years of age and older with:

- Invasive aspergillosis (1.1)
- Candidemia in non-neutropenics and other deep tissue Candida infections (1.2)
- Esophageal candidiasis (1.3)
- Serious fungal infections caused by Scedosporium apiospermum and Fusarium species including Fusarium solani, in patients intolerant of, or refractory to, other therapy (1.4)

2 DOSAGE AND ADMINISTRATION

- Dosage in Adults (2.3)

Infection | Loading dose | Maintenance Dose
Infection | Intravenous infusion | Intravenous infusion | Oral tablets | Oral suspension
Invasive Aspergillosis | 6 mg/kg every 12 hours for the first 24 hours | 4 mg/kg every 12 hours | 200 mg every 12 hours | 5 mL every 12 hours
Candidemia in nonneutropenics and other deep tissue Candida infections | 6 mg/kg every 12 hours for the first 24 hours | 3–4 mg/kg every 12 hours | 200 mg every 12 hours | 5 mL every 12 hours
Scedosporiosis and Fusariosis | 6 mg/kg every 12 hours for the first 24 hours | 4 mg/kg every 12 hours | 200 mg every 12 hours | 5 mL every 12 hours
Esophageal Candidiasis | Not Evaluated | Not Evaluated | 200 mg every 12 hours | 5 mL every 12 hours

- Adult patients weighing less than 40 kg: oral maintenance dose 100 mg or 150 mg every 12 hours
- Hepatic Impairment: Use half the maintenance dose in adult patients with mild to moderate hepatic impairment (Child-Pugh Class A and B) (2.5)
- Renal Impairment: Avoid intravenous administration in adult patients with moderate to severe renal impairment (creatinine clearance <50 mL/min) (2.6)

- Dosage in Pediatric Patients 2 years of age and older (2.4)
- For pediatric patients 2 to less than 12 years of age and 12 to 14 years of age weighing less than 50 kg see Table below.

Infection | Loading Dose | Maintenance Dose
Infection | Intravenous infusion | Intravenous infusion | Oral tablets | Oral suspension
Invasive Aspergillosis | 9 mg/kg every 12 hours for the first 24 hours | 8 mg/kg every 12 hours after the first 24 hours | 9 mg/kg every 12 hours (maximum dose of 350 mg every 12 hours) | 0.225 mL/kg every 12 hours [maximum dose of 8.75 mL (350 mg) every 12 hours]
Candidemia in nonneutropenics and other deep tissue Candida infections | 9 mg/kg every 12 hours for the first 24 hours | 8 mg/kg every 12 hours after the first 24 hours | 9 mg/kg every 12 hours (maximum dose of 350 mg every 12 hours) | 0.225 mL/kg every 12 hours [maximum dose of 8.75 mL (350 mg) every 12 hours]
Scedosporiosis and Fusariosis | 9 mg/kg every 12 hours for the first 24 hours | 8 mg/kg every 12 hours after the first 24 hours | 9 mg/kg every 12 hours (maximum dose of 350 mg every 12 hours) | 0.225 mL/kg every 12 hours [maximum dose of 8.75 mL (350 mg) every 12 hours]
Esophageal Candidiasis | Not Evaluated | 4 mg/kg every 12 hours | 9 mg/kg every 12 hours (maximum dose of 350 mg every 12 hours) | 0.225 mL/kg every 12 hours; [maximum dose of 8.75 mL (350 mg) every 12 hours]

- For pediatric patients aged 12 to 14 years weighing greater than or equal to 50 kg and those aged 15 years and older regardless of body weight use adult dosage. (2.4)
- Dosage adjustment of VFEND in pediatric patients with renal or hepatic impairment has not been established (2.5, 2.6)
- See full prescribing information for instructions on reconstitution of VFEND lyophilized powder for intravenous use and reconstitution of VFEND oral suspension and important administration instructions (2.1, 2.6, 2.7)

3 DOSAGE FORMS AND STRENGTHS

- Tablets: 50 mg, 200 mg (3)
- For Oral Suspension: 40 mg/mL (200 mg/5 mL) when reconstituted (3)
- For Injection: Lyophilized powder containing 200 mg of voriconazole and 3,200 mg of sulfobutyl ether beta-cyclodextrin sodium (SBECD); after reconstitution 10 mg/mL of voriconazole and 160 mg/mL of SBECD (3)

4 CONTRAINDICATIONS

- Known hypersensitivity to voriconazole or its excipients (4)
- Concomitant use with drugs that are highly dependent on CYP3A4 for metabolism, and for which elevated plasma concentrations are associated with serious and/or life-threatening reactions (4, 7)
- Concomitant use with drugs and herbal products that induce CYP2C19, CYP2C9, and/or CYP3A4 and for which significantly reduced voriconazole plasma concentrations may be associated with loss of efficacy (4, 7)

5 WARNINGS AND PRECAUTIONS

- Hepatic Toxicity: Serious hepatic reactions reported. Evaluate liver function tests at start of and during VFEND therapy (5.1)
- Arrhythmias and QT Prolongation: Correct potassium, magnesium and calcium prior to use; caution patients with proarrhythmic conditions (5.2)
- Infusion Related Reactions (including anaphylaxis): Stop the infusion (5.3)
- Visual Disturbances (including optic neuritis and papilledema): Monitor visual function if treatment continues beyond 28 days (5.4)
- Severe Cutaneous Adverse Reactions: Discontinue for exfoliative cutaneous reactions (5.5)
- Photosensitivity: Avoid sunlight due to risk of photosensitivity (5.6)
- Adrenal Dysfunction: Carefully monitor patients receiving VFEND and corticosteroids (via all routes of administration) for adrenal dysfunction both during and after VFEND treatment. Instruct patients to seek immediate medical care if they develop signs and symptoms of Cushing's syndrome or adrenal insufficiency (5.8)
- Embryo-Fetal Toxicity: Voriconazole can cause fetal harm when administered to a pregnant woman. Inform pregnant patients of the potential hazard to the fetus. Advise females of reproductive potential to use effective contraception during treatment with VFEND (5.9, 8.1, 8.3)
- Skeletal Adverse Reactions: Fluorosis and periostitis with long-term voriconazole therapy. Discontinue if these adverse reactions occur (5.12)
- Clinically Significant Drug Interactions: Review patient's concomitant medications (5.13, 7)
- Patients with Hereditary Galactose Intolerance, Lapp Lactase Deficiency or Glucose-Galactose Malabsorption: VFEND tablets should not be given to these patients because it contains lactose (5.14)

6 ADVERSE REACTIONS

- Adult Patients: The most common adverse reactions (incidence ≥2%) were visual disturbances, fever, nausea, rash, vomiting, chills, headache, liver function test abnormal, tachycardia, hallucinations (6)
- Pediatric Patients: The most common adverse reactions (incidence ≥5%) were visual disturbances, pyrexia, vomiting, epistaxis, nausea, rash, abdominal pain, diarrhea, hypertension, hypokalemia, cough, headache, thrombocytopenia, ALT abnormal, hypotension, peripheral edema, hyperglycemia, tachycardia, dyspnea, hypocalcemia, hypophosphatemia, LFT abnormal, mucosal inflammation, photophobia, abdominal distention, constipation, dizziness, hallucinations, hemoptysis, hypoalbuminemia, hypomagnesemia, renal impairment, upper respiratory tract infection (6)

To report SUSPECTED ADVERSE REACTIONS, contact Pfizer Inc. at 1-800-438-1985 or FDA at 1-800-FDA-1088 or www.fda.gov/medwatch.

7 DRUG INTERACTIONS

- CYP3A4, CYP2C9, and CYP2C19 inhibitors and inducers: Adjust VFEND dosage and monitor for adverse reactions or lack of efficacy (4, 7)
- VFEND may increase the concentrations and activity of drugs that are CYP3A4, CYP2C9 and CYP2C19 substrates. Reduce dosage of these other drugs and monitor for adverse reactions (4, 7)
- Phenytoin or Efavirenz: With coadministration, increase maintenance oral and intravenous dosage of VFEND (2.3, 2.7, 7)

8 USE IN SPECIFIC POPULATIONS

- Pediatrics: Safety and effectiveness in patients younger than 2 years has not been established (8.4)

FULL PRESCRIBING INFORMATION

1 INDICATIONS AND USAGE

1.1 Invasive Aspergillosis

VFEND is indicated in adults and pediatric patients (2 years of age and older) for the treatment of invasive aspergillosis (IA). In clinical trials, the majority of isolates recovered were Aspergillus fumigatus. There was a small number of cases of culture-proven disease due to species of Aspergillus other than A. fumigatus [see Clinical Studies (14.1, 14.5) and Microbiology (12.4)].

1.2 Candidemia in Non-neutropenic Patients and Other Deep Tissue Candida Infections

VFEND is indicated in adults and pediatric patients (2 years of age and older) for the treatment of candidemia in non-neutropenic patients and the following Candida infections: disseminated infections in skin and infections in abdomen, kidney, bladder wall, and wounds [see Clinical Studies (14.2, 14.5) and Microbiology (12.4)].

1.3 Esophageal Candidiasis

VFEND is indicated in adults and pediatric patients (2 years of age and older) for the treatment of esophageal candidiasis (EC) [see Clinical Studies (14.3, 14.5) and Microbiology (12.4)].

1.4 Scedosporiosis and Fusariosis

VFEND is indicated for the treatment of serious fungal infections caused by Scedosporium apiospermum (asexual form of Pseudallescheria boydii) and Fusarium spp. including Fusarium solani, in adults and pediatric patients (2 years of age and older) intolerant of, or refractory to, other therapy [see Clinical Studies (14.4) and Microbiology (12.4)].

1.5 Usage

Specimens for fungal culture and other relevant laboratory studies (including histopathology) should be obtained prior to therapy to isolate and identify causative organism(s). Therapy may be instituted before the results of the cultures and other laboratory studies are known. However, once these results become available, antifungal therapy should be adjusted accordingly.

2 DOSAGE AND ADMINISTRATION

2.1 Important Administration Instructions for Use in All Patients

Administer VFEND Tablets or Oral Suspension at least one hour before or after a meal.

VFEND I.V. for Injection requires reconstitution to 10 mg/mL and subsequent dilution to 5 mg/mL or less prior to administration as an infusion, at a maximum rate of 3 mg/kg per hour over 1 to 3 hours.

Administer diluted VFEND I.V. by intravenous infusion over 1 to 3 hours only. Do not administer as an IV bolus injection.

2.2 Use of VFEND I.V. With Other Parenteral Drug Products

Blood products and concentrated electrolytes

VFEND I.V. must not be infused concomitantly with any blood product or short-term infusion of concentrated electrolytes, even if the two infusions are running in separate intravenous lines (or cannulas). Electrolyte disturbances such as hypokalemia, hypomagnesemia and hypocalcemia should be corrected prior to initiation of and during VFEND therapy [see Warnings and Precautions (5.10)].

Intravenous solutions containing (non-concentrated) electrolytes

VFEND I.V. can be infused at the same time as other intravenous solutions containing (non-concentrated) electrolytes, but must be infused through a separate line.

Total parenteral nutrition (TPN)

VFEND I.V. can be infused at the same time as total parenteral nutrition, but must be infused in a separate line. If infused through a multiple-lumen catheter, TPN needs to be administered using a different port from the one used for VFEND I.V.

2.3 Recommended Dosing Regimen in Adults

Invasive aspergillosis and serious fungal infections due to Fusarium spp. and Scedosporium apiospermum

See Table 1. Therapy must be initiated with the specified loading dose regimen of intravenous VFEND on Day 1 followed by the recommended maintenance dose (RMD) regimen. Intravenous treatment should be continued for at least 7 days. Once the patient has clinically improved and can tolerate medication given by mouth, the oral tablet form or oral suspension form of VFEND may be utilized. The recommended oral maintenance dose of 200 mg achieves a voriconazole exposure similar to 3 mg/kg intravenously; a 300 mg oral dose achieves an exposure similar to 4 mg/kg intravenously [see Clinical Pharmacology (12.3)].

Candidemia in non-neutropenic patients and other deep tissue Candida infections

See Table 1. Patients should be treated for at least 14 days following resolution of symptoms or following last positive culture, whichever is longer.

Esophageal Candidiasis

See Table 1. Patients should be treated for a minimum of 14 days and for at least 7 days following resolution of symptoms.

Table 1: Recommended Dosing Regimen (Adults)
Infection | Loading Dose | Maintenance Dose [Increase dose when VFEND is coadministered with phenytoin or efavirenz (7); Decrease dose in patients with hepatic impairment (2.5)] , [In healthy volunteer studies, the 200 mg oral every 12 hours dose provided an exposure (AUCτ) similar to a 3 mg/kg intravenous infusion every 12 hours dose; the 300 mg oral every 12 hours dose provided an exposure (AUCτ) similar to a 4 mg/kg intravenous infusion every 12 hours dose (12).]
 | Intravenous infusion | Intravenous infusion | Oral tablets [Adult patients who weigh less than 40 kg should receive half of the oral maintenance dose.] | Oral suspension
Invasive Aspergillosis [In a clinical study of IA, the median duration of intravenous VFEND therapy was 10 days (range 2 to 85 days). The median duration of oral VFEND therapy was 76 days (range 2 to 232 days) (14.1).] | 6 mg/kg every 12 hours for the first 24 hours | 4 mg/kg every 12 hours | 200 mg every 12 hours | 5 mL every 12 hours
Candidemia in nonneutropenic patients and other deep tissue Candida infections | 6 mg/kg every 12 hours for the first 24 hours | 3–4 mg/kg every 12 hours [In clinical trials, patients with candidemia received 3 mg/kg intravenous infusion every 12 hours as primary therapy, while patients with other deep tissue Candida infections received 4 mg/kg every 12 hours as salvage therapy. Appropriate dose should be based on the severity and nature of the infection.] | 200 mg every 12 hours | 5 mL every 12 hours
Esophageal Candidiasis | Not Evaluated [Not evaluated in patients with EC.] | Not Evaluated | 200 mg every 12 hours | 5 mL every 12 hours
Scedosporiosis and Fusariosis | 6 mg/kg every 12 hours for the first 24 hours | 4 mg/kg every 12 hours | 200 mg every 12 hours | 5 mL every 12 hours

Method for Adjusting the Dosing Regimen in Adults

- If the patient’s response is inadequate, the oral maintenance dose for VFEND tablets or oral suspension may be increased from 200 mg (or 5 mL) every 12 hours to 300 mg (or 7.5 mL) every 12 hours.
- For adult patients weighing less than 40 kg, the oral maintenance dose for VFEND tablets or oral suspension may be increased from 100 mg (or 2.5 mL) every 12 hours to 150 mg (or 3.75 mL) every 12 hours.
- If the patient is unable to tolerate 300 mg (or 7.5 mL) orally every 12 hours, reduce the oral maintenance dose of VFEND tablets or oral suspension by 50 mg (or 1.25 mL) steps to a minimum of 200 mg (or 5 mL) every 12 hours for adult patients weighing more than 40 kg or to 100 mg (or 2.5 mL) every 12 hours for adult patients weighing less than 40 kg.
- If the patient is unable to tolerate 4 mg/kg intravenously every 12 hours, reduce the intravenous maintenance dose to 3 mg/kg every 12 hours.

2.4 Recommended Dosing Regimen in Pediatric Patients

The recommended dosing regimen for pediatric patients 2 to less than 12 years of age and 12 to 14 years of age with body weight less than 50 kg is shown in Table 2. For pediatric patients 12 to 14 years of age with a body weight greater than or equal to 50 kg and those 15 years of age and above regardless of body weight, administer the adult dosing regimen of VFEND [see Dosage and Administration (2.3)].

Table 2: Recommended Dosing Regimen for Pediatric Patients 2 to less than 12 years of age and 12 to 14 years of age with body weight less than 50 kg [Based on a population pharmacokinetic analysis in 112 immunocompromised pediatric patients aged 2 to less than 12 years of age and 26 immunocompromised pediatric patients aged 12 to less than 17 years of age.]
 | Loading Dose | Maintenance Dose
 | Intravenous infusion | Intravenous infusion | Oral tablets | Oral suspension
Invasive Aspergillosis [In the Phase 3 clinical trials, patients with IA received intravenous (IV) treatment for at least 6 weeks and up to a maximum of 12 weeks. Patients received IV treatment for at least the first 7 days of therapy and then could be switched to oral VFEND therapy.] | 9 mg/kg every 12 hours for the first 24 hours | 8 mg/kg every 12 hours after the first 24 hours | 9 mg/kg every 12 hours (maximum dose of 350 mg every 12 hours) | 0.225 mL/kg every 12 hours [maximum dose of 8.75 mL (350 mg) every 12 hours]
Candidemia in nonneutropenics and other deep tissue Candida infections [Study treatment for primary or salvage invasive candidiasis and candidemia (ICC) or EC consisted of intravenous VFEND, with an option to switch to oral therapy after at least 5 days of IV therapy, based on subjects meeting switch criteria. For subjects with primary or salvage ICC, VFEND was administered for at least 14 days after the last positive culture. A maximum of 42 days of treatment was permitted. Patients with primary or salvage EC were treated for at least 7 days after the resolution of clinical signs and symptoms. A maximum of 42 days of treatment was permitted.] | 9 mg/kg every 12 hours for the first 24 hours | 8 mg/kg every 12 hours after the first 24 hours | 9 mg/kg every 12 hours (maximum dose of 350 mg every 12 hours) | 0.225 mL/kg every 12 hours [maximum dose of 8.75 mL (350 mg) every 12 hours]
Scedosporiosis and Fusariosis | 9 mg/kg every 12 hours for the first 24 hours | 8 mg/kg every 12 hours after the first 24 hours | 9 mg/kg every 12 hours (maximum dose of 350 mg every 12 hours) | 0.225 mL/kg every 12 hours [maximum dose of 8.75 mL (350 mg) every 12 hours]
Esophageal Candidiasis | Not Evaluated | 4 mg/kg every 12 hours | 9 mg/kg every 12 hours (maximum dose of 350 mg every 12 hours) | 0.225 mL/kg every 12 hours [maximum dose of 8.75 mL (350 mg) every 12 hours]

Initiate therapy with an intravenous infusion regimen. Consider an oral regimen only after there is a significant clinical improvement. Note that an 8 mg/kg intravenous dose will provide voriconazole exposure approximately 2-fold higher than a 9 mg/kg oral dose.

The oral dose recommendation for children is based on studies in which VFEND was administered as the powder for oral suspension formulation. Bioequivalence between the VFEND powder for oral suspension and VFEND tablets has not been investigated in a pediatric population.

Oral bioavailability may be limited in pediatric patients 2 to 12 years with malabsorption and very low body weight for age. In that case, intravenous VFEND administration is recommended.

Method for Adjusting the Dosing Regimen in Pediatric Patients

Pediatric Patients 2 to less than 12 years of age and 12 to 14 years of age with body weight less than 50 kg

If patient response is inadequate and the patient is able to tolerate the initial intravenous maintenance dose, the maintenance dose may be increased by 1 mg/kg steps. If patient response is inadequate and the patient is able to tolerate the oral maintenance dose, the dose may be increased by 1 mg/kg (0.025 mL/kg) steps or 50 mg (1.25 mL) steps to a maximum of 350 mg (8.75 mL) every 12 hours. If patients are unable to tolerate the initial intravenous maintenance dose, reduce the dose by 1 mg/kg steps. If patients are unable to tolerate the oral maintenance dose, reduce the dose by 1 mg/kg (0.025 mL/kg) or 50 mg (1.25 mL) steps.

Pediatric patients 12 to 14 years of age weighing greater than or equal to 50 kg and 15 years of age and older regardless of body weight:

Use the optimal method for titrating dosage recommended for adults [see Dosage and Administration (2.3)].

2.5 Dosage Modifications in Patients With Hepatic Impairment

Adults

The maintenance dose of VFEND should be reduced in adult patients with mild to moderate hepatic impairment, Child-Pugh Class A and B. There are no PK data to allow for dosage adjustment recommendations in patients with severe hepatic impairment (Child-Pugh Class C).

Duration of therapy should be based on the severity of the patient's underlying disease, recovery from immunosuppression, and clinical response.

Adult patients with baseline liver function tests (ALT, AST) of up to 5 times the upper limit of normal (ULN) were included in the clinical program. Dose adjustments are not necessary for adult patients with this degree of abnormal liver function, but continued monitoring of liver function tests for further elevations is recommended [see Warnings and Precautions (5.1)].

It is recommended that the recommended VFEND loading dose regimens be used, but that the maintenance dose be halved in adult patients with mild to moderate hepatic cirrhosis (Child-Pugh Class A and B) [see Clinical Pharmacology (12.3)].

VFEND has not been studied in adult patients with severe hepatic cirrhosis (Child-Pugh Class C) or in patients with chronic hepatitis B or chronic hepatitis C disease. VFEND has been associated with elevations in liver function tests and with clinical signs of liver damage, such as jaundice. VFEND should only be used in patients with severe hepatic impairment if the benefit outweighs the potential risk. Patients with hepatic impairment must be carefully monitored for drug toxicity.

Pediatric Patients

Dosage adjustment of VFEND in pediatric patients with hepatic impairment has not been established [see Use in Specific Populations (8.4)].

2.6 Dosage Modifications in Patients With Renal Impairment

Adult Patients

The pharmacokinetics of orally administered VFEND are not significantly affected by renal impairment. Therefore, no adjustment is necessary for oral dosing in patients with mild to severe renal impairment [see Clinical Pharmacology (12.3)].

In patients with moderate or severe renal impairment (creatinine clearance <50 mL/min) who are receiving an intravenous infusion of VFEND, accumulation of the intravenous vehicle, SBECD, occurs. Oral voriconazole should be administered to these patients, unless an assessment of the benefit/risk to the patient justifies the use of intravenous VFEND. Serum creatinine levels should be closely monitored in these patients, and, if increases occur, consideration should be given to changing to oral VFEND therapy [see Warnings and Precautions (5.7)].

Voriconazole and the intravenous vehicle, SBECD, are dialyzable. A 4-hour hemodialysis session does not remove a sufficient amount of voriconazole to warrant dose adjustment [see Clinical Pharmacology (12.3)].

Pediatric Patients

Dosage adjustment of VFEND in pediatric patients with renal impairment has not been established [see Use in Specific Populations (8.4)].

2.7 Dosage Adjustment When Coadministered With Phenytoin or Efavirenz

The maintenance dose of voriconazole should be increased when coadministered with phenytoin or efavirenz. Use the optimal method for titrating dosage [see Drug Interactions (7) and Dosage and Administration (2.3)].

2.8 Preparation and Intravenous Administration of VFEND for Injection

Reconstitution

The powder is reconstituted with 19 mL of Water For Injection to obtain an extractable volume of 20 mL of clear concentrate containing 10 mg/mL of voriconazole. It is recommended that a standard 20 mL (non-automated) syringe be used to ensure that the exact amount (19.0 mL) of Water for Injection is dispensed. Discard the vial if a vacuum does not pull the diluent into the vial. Shake the vial until all the powder is dissolved.

Dilution

VFEND must be infused over 1 to 3 hours, at a concentration of 5 mg/mL or less. Therefore, the required volume of the 10 mg/mL VFEND concentrate should be further diluted as follows (appropriate diluents listed below):

1. Calculate the volume of 10 mg/mL VFEND concentrate required based on the patient's weight (see Table 3).
2. In order to allow the required volume of VFEND concentrate to be added, withdraw and discard at least an equal volume of diluent from the infusion bag or bottle to be used. The volume of diluent remaining in the bag or bottle should be such that when the 10 mg/mL VFEND concentrate is added, the final concentration is not less than 0.5 mg/mL nor greater than 5 mg/mL.
3. Using a suitable size syringe and aseptic technique, withdraw the required volume of VFEND concentrate from the appropriate number of vials and add to the infusion bag or bottle. Discard Partially Used Vials.

The final VFEND solution must be infused over 1 to 3 hours at a maximum rate of 3 mg/kg per hour.

Table 3: Required Volumes of 10 mg/mL VFEND Concentrate
Body Weight (kg) | Volume of VFEND Concentrate (10 mg/mL) required for:
Body Weight (kg) | 3 mg/kg dose (number of vials) | 4 mg/kg dose (number of vials) | 6 mg/kg dose (number of vials) | 8 mg/kg dose (number of vials) | 9 mg/kg dose (number of vials)
10 | - | 4 mL (1) | - | 8 mL (1) | 9 mL (1)
15 | - | 6 mL (1) | - | 12 mL (1) | 13.5 mL (1)
20 | - | 8 mL (1) | - | 16 mL (1) | 18 mL (1)
25 | - | 10 mL (1) | - | 20 mL (1) | 22.5 mL (2)
30 | 9 mL (1) | 12 mL (1) | 18 mL (1) | 24 mL (2) | 27 mL (2)
35 | 10.5 mL (1) | 14 mL (1) | 21 mL (2) | 28 mL (2) | 31.5 mL (2)
40 | 12 mL (1) | 16 mL (1) | 24 mL (2) | 32 mL (2) | 36 mL (2)
45 | 13.5 mL (1) | 18 mL (1) | 27 mL (2) | 36 mL (2) | 40.5 mL (3)
50 | 15 mL (1) | 20 mL (1) | 30 mL (2) | 40 mL (2) | 45 mL (3)
55 | 16.5 mL (1) | 22 mL (2) | 33 mL (2) | 44 mL (3) | 49.5 mL (3)
60 | 18 mL (1) | 24 mL (2) | 36 mL (2) | 48 mL (3) | 54 mL (3)
65 | 19.5 mL (1) | 26 mL (2) | 39 mL (2) | 52 mL (3) | 58.5 mL (3)
70 | 21 mL (2) | 28 mL (2) | 42 mL (3) | - | -
75 | 22.5 mL (2) | 30 mL (2) | 45 mL (3) | - | -
80 | 24 mL (2) | 32 mL (2) | 48 mL (3) | - | -
85 | 25.5 mL (2) | 34 mL (2) | 51 mL (3) | - | -
90 | 27 mL (2) | 36 mL (2) | 54 mL (3) | - | -
95 | 28.5 mL (2) | 38 mL (2) | 57 mL (3) | - | -
100 | 30 mL (2) | 40 mL (2) | 60 mL (3) | - | -

VFEND I.V. for Injection is a single-dose unpreserved sterile lyophile. Therefore, from a microbiological point of view, once reconstituted, the product should be used immediately. If not used immediately, in-use storage times and conditions prior to use are the responsibility of the user and should not be longer than 24 hours at 2°C to 8°C (36°F to 46°F). This medicinal product is for single use only and any unused solution should be discarded. Only clear solutions without particles should be used.

The reconstituted solution can be diluted with:

0.9% Sodium Chloride USP
Lactated Ringers USP
5% Dextrose and Lactated Ringers USP
5% Dextrose and 0.45% Sodium Chloride USP
5% Dextrose USP
5% Dextrose and 20 mEq Potassium Chloride USP
0.45% Sodium Chloride USP
5% Dextrose and 0.9% Sodium Chloride USP

The compatibility of VFEND I.V. with diluents other than those described above is unknown (see Incompatibilities below).

Parenteral drug products should be inspected visually for particulate matter and discoloration prior to administration, whenever solution and container permit.

Incompatibilities

VFEND I.V. must not be diluted with 4.2% Sodium Bicarbonate Infusion. The mildly alkaline nature of this diluent caused slight degradation of VFEND after 24 hours storage at room temperature. Although refrigerated storage is recommended following reconstitution, use of this diluent is not recommended as a precautionary measure. Compatibility with other concentrations is unknown.

2.9 Preparation and Administration of VFEND Oral Suspension

Reconstitution

Tap the bottle to release the powder. Add 46 mL of water to the bottle. Shake the closed bottle vigorously for about 1 minute. Remove child-resistant cap and push bottle adaptor into the neck of the bottle. Replace the cap. Write the date of expiration of the reconstituted suspension on the bottle label (the shelf-life of the reconstituted suspension is 14 days at controlled room temperature 15°C to 30°C [59°F to 86°F]).

Instructions for use

Shake the closed bottle of reconstituted suspension for approximately 10 seconds before each use. The reconstituted oral suspension should only be administered using the oral dispenser supplied with each pack.

Incompatibilities

VFEND for Oral Suspension and the 40 mg/mL reconstituted oral suspension should not be mixed with any other medication or additional flavoring agent. It is not intended that the suspension be further diluted with water or other vehicles.

3 DOSAGE FORMS AND STRENGTHS

Powder for Solution for Injection

VFEND I.V. for Injection is supplied in a single-dose vial as a sterile lyophilized powder equivalent to 200 mg voriconazole and 3,200 mg sulfobutyl ether beta-cyclodextrin sodium (SBECD).

Tablets

VFEND 50 mg tablets; white, film-coated, round, debossed with "Pfizer" on one side and "VOR50" on the reverse.

VFEND 200 mg tablets; white, film-coated, capsule shaped, debossed with "Pfizer" on one side and "VOR200" on the reverse.

Powder for Oral Suspension

VFEND for Oral Suspension is supplied as a white to off-white powder in 100 mL high density polyethylene (HDPE) bottles. Following reconstitution, the volume of white to off white suspension is 75 mL, providing a usable volume of 70 mL. Each mL of the oral suspension contains 40 mg of voriconazole (200 mg of voriconazole per 5 mL).

4 CONTRAINDICATIONS

- VFEND is contraindicated in patients with known hypersensitivity to voriconazole or its excipients [see Warnings and Precautions (5.5) and Adverse Reactions (6.1, 6.2)]. There is no information regarding cross-sensitivity between VFEND and other azole antifungal agents. Refer to the prescribing information for other azole antifungal agents.
- Concomittant use of VFEND with the interacting drugs described and listed below in this section are a guide and not considered a comprehensive list of all possible drugs that may be contraindicated with VFEND.
  1. Concomitant use of VFEND is contraindicated with drugs that are highly dependent on CYP3A4 for metabolism, and for which elevated plasma concentrations are associated with serious and/or life-threatening reactions [see Drug Interactions (7)]:
    1. Eplerenone
    2. Ergot alkaloids (e.g., ergotamine, dihydroergotamine)
    3. Finerenone
    4. Ivabradine
    5. Lurasidone
    6. Naloxegol
    7. Pimozide
    8. Quinidine
    9. Rifabutin [see Clinical Pharmacology (12.3)]
    10. Sirolimus [see Clinical Pharmacology (12.3)]
    11. Tolvaptan
    12. Venetoclax: Coadministration at initiation and during the ramp-up phase is contraindicated in patients with chronic lymphocytic leukemia (CLL) or small lymphocytic lymphoma (SLL) due to the potential for increased risk of tumor lysis syndrome [see Drug Interactions (7)].
    13. Voclosporin
  2. Concomitant use of VFEND is contraindicated with drugs and herbal products that induce CYP2C19, CYP2C9, and/or CYP3A4 and for which significantly reduced voriconazole plasma concentrations may be associated with loss of efficacy [see Drug Interactions (7)]:
    1. Carbamazepine
    2. Efavirenz
      Concomitant use with efavirenz dosages of 400 mg every 24 hours or higher is contraindicated [see Clinical Pharmacology (12.3)].
    3. Long-acting barbiturates
    4. Rifabutin
    5. Rifampin
    6. Ritonavir
      Concomitant use with high-dose ritonavir (400 mg every 12 hours) is contraindicated. Concomitant use with low-dose ritonavir (100 mg every 12 hours) should be avoided, unless an assessment of the benefit/risk to the patient justifies the use of VFEND [see Clinical Pharmacology (12.3)].
    7. St. John’s Wort [see Clinical Pharmacology (12.3)]

5 WARNINGS AND PRECAUTIONS

5.1 Hepatic Toxicity

In clinical trials, there have been uncommon cases of serious hepatic reactions during treatment with VFEND (including clinical hepatitis, cholestasis and fulminant hepatic failure, including fatalities). Instances of hepatic reactions were noted to occur primarily in patients with serious underlying medical conditions (predominantly hematological malignancy). Hepatic reactions, including hepatitis and jaundice, have occurred among patients with no other identifiable risk factors. Liver dysfunction has usually been reversible on discontinuation of therapy [see Adverse Reactions (6.1)].

A higher frequency of liver enzyme elevations was observed in the pediatric population [see Adverse Reactions (6.1)]. Hepatic function should be monitored in both adult and pediatric patients.

Measure serum transaminase levels and bilirubin at the initiation of VFEND therapy and monitor at least weekly for the first month of treatment. Monitoring frequency can be reduced to monthly during continued use if no clinically significant changes are noted. If liver function tests become markedly elevated compared to baseline, VFEND should be discontinued unless the medical judgment of the benefit/risk of the treatment for the patient justifies continued use [see Dosage and Administration (2.5) and Adverse Reactions (6.1)].

5.2 Arrhythmias and QT Prolongation

Some azoles, including VFEND, have been associated with prolongation of the QT interval on the electrocardiogram. During clinical development and postmarketing surveillance, there have been rare cases of arrhythmias, (including ventricular arrhythmias such as torsade de pointes), cardiac arrests and sudden deaths in patients taking voriconazole. These cases usually involved seriously ill patients with multiple confounding risk factors, such as history of cardiotoxic chemotherapy, cardiomyopathy, hypokalemia and concomitant medications that may have been contributory.

VFEND should be administered with caution to patients with potentially proarrhythmic conditions, such as:

- Congenital or acquired QT prolongation
- Cardiomyopathy, in particular when heart failure is present
- Sinus bradycardia
- Existing symptomatic arrhythmias
- Concomitant medicinal product that is known to prolong QT interval [see Contraindications (4), Drug Interactions (7), and Clinical Pharmacology (12.3)]

Rigorous attempts to correct potassium, magnesium and calcium should be made before starting and during voriconazole therapy [see Clinical Pharmacology (12.3)].

5.3 Infusion Related Reactions

During infusion of the intravenous formulation of VFEND in healthy subjects, anaphylactoid-type reactions, including flushing, fever, sweating, tachycardia, chest tightness, dyspnea, faintness, nausea, pruritus and rash, have occurred uncommonly. Symptoms appeared immediately upon initiating the infusion. Consideration should be given to stopping the infusion should these reactions occur.

5.4 Visual Disturbances

The effect of VFEND on visual function is not known if treatment continues beyond 28 days. There have been postmarketing reports of prolonged visual adverse reactions, including optic neuritis and papilledema. If treatment continues beyond 28 days, visual function including visual acuity, visual field, and color perception should be monitored [see Adverse Reactions (6.2)].

5.5 Severe Cutaneous Adverse Reactions

Severe cutaneous adverse reactions (SCARs), such as Stevens-Johnson syndrome (SJS), toxic epidermal necrolysis (TEN), and drug reaction with eosinophilia and systemic symptoms (DRESS), which can be life-threatening or fatal, have been reported during treatment with VFEND. If a patient develops a severe cutaneous adverse reaction, VFEND should be discontinued [see Adverse Reactions (6.1, 6.2)].

5.6 Photosensitivity

VFEND has been associated with photosensitivity skin reaction. Patients, including pediatric patients, should avoid exposure to direct sunlight during VFEND treatment and should use measures such as protective clothing and sunscreen with high sun protection factor (SPF). If phototoxic reactions occur, the patient should be referred to a dermatologist and VFEND discontinuation should be considered. If VFEND is continued despite the occurrence of phototoxicity-related lesions, dermatologic evaluation should be performed on a systematic and regular basis to allow early detection and management of premalignant lesions. Squamous cell carcinoma of the skin (including cutaneous SCC in situ, or Bowen's disease) and melanoma have been reported during long-term VFEND therapy in patients with photosensitivity skin reactions. If a patient develops a skin lesion consistent with premalignant skin lesions, squamous cell carcinoma or melanoma, VFEND should be discontinued. In addition, VFEND has been associated with photosensitivity related skin reactions such as pseudoporphyria, cheilitis, and cutaneous lupus erythematosus, as well as increased risk of skin toxicity with concomitant use of methotrexate, a drug associated with ultraviolet (UV) reactivation. There is the potential for this risk to be observed with other drugs associated with UV reactivation. Patients should avoid strong, direct sunlight during VFEND therapy.

The frequency of phototoxicity reactions is higher in the pediatric population. Because squamous cell carcinoma has been reported in patients who experience photosensitivity reactions, stringent measures for photoprotection are warranted in children. In children experiencing photoaging injuries such as lentigines or ephelides, sun avoidance and dermatologic follow-up are recommended even after treatment discontinuation.

5.7 Renal Toxicity

Acute renal failure has been observed in patients undergoing treatment with VFEND. Patients being treated with voriconazole are likely to be treated concomitantly with nephrotoxic medications and may have concurrent conditions that may result in decreased renal function.

Patients should be monitored for the development of abnormal renal function. This should include laboratory evaluation of serum creatinine [see Clinical Pharmacology (12.3) and Dosage and Administration (2.6)].

5.8 Adrenal Dysfunction

Reversible cases of azole-induced adrenal insufficiency have been reported in patients receiving azoles, including VFEND. Adrenal insufficiency has been reported in patients receiving azoles with or without concomitant corticosteroids. In patients receiving azoles without corticosteroids adrenal insufficiency is related to direct inhibition of steroidogenesis by azoles. In patients taking corticosteroids, voriconazole associated CYP3A4 inhibition of their metabolism may lead to corticosteroid excess and adrenal suppression [see Drug Interactions (7) and Clinical Pharmacology (12.3)]. Cushing's syndrome with and without subsequent adrenal insufficiency has also been reported in patients receiving VFEND concomitantly with corticosteroids.

Patients receiving VFEND and corticosteroids (via all routes of administration) should be carefully monitored for adrenal dysfunction both during and after VFEND treatment. Patients should be instructed to seek immediate medical care if they develop signs and symptoms of Cushing's syndrome or adrenal insufficiency.

5.9 Embryo-Fetal Toxicity

Voriconazole can cause fetal harm when administered to a pregnant woman.

In animals, voriconazole administration was associated with fetal malformations, embryotoxicity, increased gestational length, dystocia and embryomortality [see Use in Specific Populations (8.1)].

If VFEND is used during pregnancy, or if the patient becomes pregnant while taking VFEND, inform the patient of the potential hazard to the fetus. Advise females of reproductive potential to use effective contraception during treatment with VFEND [see Use in Specific Populations (8.3)].

5.10 Laboratory Tests

Electrolyte disturbances such as hypokalemia, hypomagnesemia and hypocalcemia should be corrected prior to initiation of and during VFEND therapy.

Patient management should include laboratory evaluation of renal (particularly serum creatinine) and hepatic function (particularly liver function tests and bilirubin).

5.11 Pancreatitis

Pancreatitis has been observed in patients undergoing treatment with VFEND [see Adverse Reactions (6.1, 6.2)] Patients with risk factors for acute pancreatitis (e.g., recent chemotherapy, hematopoietic stem cell transplantation [HSCT]) should be monitored for the development of pancreatitis during VFEND treatment.

5.12 Skeletal Adverse Reactions

Fluorosis and periostitis have been reported during long-term VFEND therapy. If a patient develops skeletal pain and radiologic findings compatible with fluorosis or periostitis, VFEND should be discontinued [see Adverse Reactions (6.2)].

5.13 Clinically Significant Drug Interactions

See Table 10 for a listing of drugs that may significantly alter voriconazole concentrations. Also, see Table 11 for a listing of drugs that may interact with voriconazole resulting in altered pharmacokinetics or pharmacodynamics of the other drug [see Contraindications (4) and Drug Interactions (7)].

5.14 Galactose Intolerance

VFEND tablets contain lactose and should not be given to patients with rare hereditary problems of galactose intolerance, Lapp lactase deficiency or glucose-galactose malabsorption.

6 ADVERSE REACTIONS

The following serious adverse reactions are described elsewhere in the labeling:

Hepatic Toxicity [see Warnings and Precautions (5.1)]

Arrhythmias and QT Prolongation [see Warnings and Precautions (5.2)]

Infusion Related Reactions [see Warnings and Precautions (5.3)]

Visual Disturbances [see Warnings and Precautions (5.4)]

Severe Cutaneous Adverse Reactions [see Warnings and Precautions (5.5)]

Photosensitivity [see Warnings and Precautions (5.6)]

Renal Toxicity [see Warnings and Precautions (5.7)]

6.1 Clinical Trials Experience

Because clinical trials are conducted under widely varying conditions, adverse reaction rates observed in clinical trials of a drug cannot be directly compared to rates in the clinical trials of another drug and may not reflect the rates observed in practice.

Clinical Trials Experience in Adults

Overview

The most frequently reported adverse reactions (see Table 4) in the adult therapeutic trials were visual disturbances (18.7%), fever (5.7%), nausea (5.4%), rash (5.3%), vomiting (4.4%), chills (3.7%), headache (3.0%), liver function test increased (2.7%), tachycardia (2.4%), hallucinations (2.4%). The adverse reactions which most often led to discontinuation of voriconazole therapy were elevated liver function tests, rash, and visual disturbances [see Warning and Precautions (5.1, 5.4) and Adverse Reactions (6.1)].

The data described in Table 4 reflect exposure to voriconazole in 1655 patients in nine therapeutic studies. This represents a heterogeneous population, including immunocompromised patients, e.g., patients with hematological malignancy or HIV and non-neutropenic patients. This subgroup does not include healthy subjects and patients treated in the compassionate use and non-therapeutic studies. This patient population was 62% male, had a mean age of 46 years (range 11–90, including 51 patients aged 12–18 years), and was 78% White and 10% Black. Five hundred sixty one patients had a duration of voriconazole therapy of greater than 12 weeks, with 136 patients receiving voriconazole for over six months. Table 4 includes all adverse reactions which were reported at an incidence of ≥2% during voriconazole therapy in the all therapeutic studies population, studies 307/602 and 608 combined, or study 305, as well as events of concern which occurred at an incidence of <2%.

In study 307/602, 381 patients (196 on voriconazole, 185 on amphotericin B) were treated to compare voriconazole to amphotericin B followed by other licensed antifungal therapy (OLAT) in the primary treatment of patients with acute IA. The rate of discontinuation from voriconazole study medication due to adverse reactions was 21.4% (42/196 patients). In study 608, 403 patients with candidemia were treated to compare voriconazole (272 patients) to the regimen of amphotericin B followed by fluconazole (131 patients). The rate of discontinuation from voriconazole study medication due to adverse reactions was 19.5% out of 272 patients. Study 305 evaluated the effects of oral voriconazole (200 patients) and oral fluconazole (191 patients) in the treatment of EC. The rate of discontinuation from voriconazole study medication in Study 305 due to adverse reactions was 7% (14/200 patients). Laboratory test abnormalities for these studies are discussed under Clinical Laboratory Values below.

Table 4: Adverse Reactions Rate ≥ 2% on Voriconazole or Adverse Reactions of Concern in Therapeutic Studies Population, Studies 307/602–608 Combined, or Study 305. Possibly Related to Therapy or Causality Unknown [Study 307/602: IA; Study 608: candidemia; Study 305: EC]
 | Therapeutic Studies [Studies 303, 304, 305, 307, 309, 602, 603, 604, 608] | Studies 307/602 and 608 (IV/ oral therapy) |  |  | Study 305 (oral therapy)
 | Voriconazole N=1655 | Voriconazole N=468 | Ampho B [Amphotericin B followed by other licensed antifungal therapy] N=185 | Ampho B→ Fluconazole N=131 | Voriconazole N=200 | Fluconazole N=191
 | N (%) | N (%) | N (%) | N (%) | N (%) | N (%)
Special Senses [See Warnings and Precautions (5.4)]
Abnormal vision | 310 (18.7) | 63 (13.5) | 1 (0.5) | 0 | 31 (15.5) | 8 (4.2)
Photophobia | 37 (2.2) | 8 (1.7) | 0 | 0 | 5 (2.5) | 2 (1.0)
Chromatopsia | 20 (1.2) | 2 (0.4) | 0 | 0 | 2 (1.0) | 0
Body as a Whole
Fever | 94 (5.7) | 8 (1.7) | 25 (13.5) | 5 (3.8) | 0 | 0
Chills | 61 (3.7) | 1 (0.2) | 36 (19.5) | 8 (6.1) | 1 (0.5) | 0
Headache | 49 (3.0) | 9 (1.9) | 8 (4.3) | 1 (0.8) | 0 | 1 (0.5)
Cardiovascular System
Tachycardia | 39 (2.4) | 6 (1.3) | 5 (2.7) | 0 | 0 | 0
Digestive System
Nausea | 89 (5.4) | 18 (3.8) | 29 (15.7) | 2 (1.5) | 2 (1.0) | 3 (1.6)
Vomiting | 72 (4.4) | 15 (3.2) | 18 (9.7) | 1 (0.8) | 2 (1.0) | 1 (0.5)
Liver function tests abnormal | 45 (2.7) | 15 (3.2) | 4 (2.2) | 1 (0.8) | 6 (3.0) | 2 (1.0)
Cholestatic jaundice | 17 (1.0) | 8 (1.7) | 0 | 1 (0.8) | 3 (1.5) | 0
Metabolic and Nutritional Systems
Alkaline phosphatase increased | 59 (3.6) | 19 (4.1) | 4 (2.2) | 3 (2.3) | 10 (5.0) | 3 (1.6)
Hepatic enzymes increased | 30 (1.8) | 11 (2.4) | 5 (2.7) | 1 (0.8) | 3 (1.5) | 0
SGOT increased | 31 (1.9) | 9 (1.9) | 0 | 1 (0.8) | 8 (4.0) | 2 (1.0)
SGPT increased | 29 (1.8) | 9 (1.9) | 1 (0.5) | 2 (1.5) | 6 (3.0) | 2 (1.0)
Hypokalemia | 26 (1.6) | 3 (0.6) | 36 (19.5) | 16 (12.2) | 0 | 0
Bilirubinemia | 15 (0.9) | 5 (1.1) | 3 (1.6) | 2 (1.5) | 1 (0.5) | 0
Creatinine increased | 4 (0.2) | 0 | 59 (31.9) | 10 (7.6) | 1 (0.5) | 0
Nervous System
Hallucinations | 39 (2.4) | 13 (2.8) | 1 (0.5) | 0 | 0 | 0
Skin and Appendages
Rash | 88 (5.3) | 20 (4.3) | 7 (3.8) | 1 (0.8) | 3 (1.5) | 1 (0.5)
Urogenital
Kidney function abnormal | 10 (0.6) | 6 (1.3) | 40 (21.6) | 9 (6.9) | 1 (0.5) | 1 (0.5)
Acute kidney failure | 7 (0.4) | 2 (0.4) | 11 (5.9) | 7 (5.3) | 0 | 0

Visual Disturbances

VFEND treatment-related visual disturbances are common. In therapeutic trials, approximately 21% of patients experienced abnormal vision, color vision change and/or photophobia. Visual disturbances may be associated with higher plasma concentrations and/or doses.

The mechanism of action of the visual disturbance is unknown, although the site of action is most likely to be within the retina. In a study in healthy subjects investigating the effect of 28-day treatment with voriconazole on retinal function, VFEND caused a decrease in the electroretinogram (ERG) waveform amplitude, a decrease in the visual field, and an alteration in color perception. The ERG measures electrical currents in the retina. These effects were noted early in administration of VFEND and continued through the course of study drug treatment. Fourteen days after the end of dosing, ERG, visual fields and color perception returned to normal [see Warnings and Precautions (5.4)].

Dermatological Reactions

Dermatological reactions were common in patients treated with VFEND. The mechanism underlying these dermatologic adverse reactions remains unknown.

Severe cutaneous adverse reactions (SCARs), including Stevens-Johnson syndrome (SJS), toxic epidermal necrolysis (TEN), and drug reaction with eosinophilia and systemic symptoms (DRESS) have been reported during treatment with VFEND. Erythema multiforme has also been reported during treatment with VFEND [see Warnings and Precautions (5.5) and Adverse Reactions (6.2)].

VFEND has also been associated with additional photosensitivity related skin reactions such as pseudoporphyria, cheilitis, and cutaneous lupus erythematosus [see Warnings and Precautions (5.6) and Adverse Reactions (6.2)].

Less Common Adverse Reactions

The following adverse reactions occurred in <2% of all voriconazole-treated patients in all therapeutic studies (N=1655). This listing includes events where a causal relationship to voriconazole cannot be ruled out or those which may help the physician in managing the risks to the patients. The list does not include events included in Table 4 above and does not include every event reported in the voriconazole clinical program.

Body as a Whole: abdominal pain, abdomen enlarged, allergic reaction, anaphylactoid reaction [see Warnings and Precautions (5.3)], ascites, asthenia, back pain, chest pain, cellulitis, edema, face edema, flank pain, flu syndrome, graft versus host reaction, granuloma, infection, bacterial infection, fungal infection, injection site pain, injection site infection/inflammation, mucous membrane disorder, multi-organ failure, pain, pelvic pain, peritonitis, sepsis, substernal chest pain.

Cardiovascular: atrial arrhythmia, atrial fibrillation, AV block complete, bigeminy, bradycardia, bundle branch block, cardiomegaly, cardiomyopathy, cerebral hemorrhage, cerebral ischemia, cerebrovascular accident, congestive heart failure, deep thrombophlebitis, endocarditis, extrasystoles, heart arrest, hypertension, hypotension, myocardial infarction, nodal arrhythmia, palpitation, phlebitis, postural hypotension, pulmonary embolus, QT interval prolonged, supraventricular extrasystoles, supraventricular tachycardia, syncope, thrombophlebitis, vasodilatation, ventricular arrhythmia, ventricular fibrillation, ventricular tachycardia (including torsade de pointes) [see Warnings and Precautions (5.2)].

Digestive: anorexia, cheilitis, cholecystitis, cholelithiasis, constipation, diarrhea, duodenal ulcer perforation, duodenitis, dyspepsia, dysphagia, dry mouth, esophageal ulcer, esophagitis, flatulence, gastroenteritis, gastrointestinal hemorrhage, GGT/LDH elevated, gingivitis, glossitis, gum hemorrhage, gum hyperplasia, hematemesis, hepatic coma, hepatic failure, hepatitis, intestinal perforation, intestinal ulcer, jaundice, enlarged liver, melena, mouth ulceration, pancreatitis, parotid gland enlargement, periodontitis, proctitis, pseudomembranous colitis, rectal disorder, rectal hemorrhage, stomach ulcer, stomatitis, tongue edema.

Endocrine: adrenal cortex insufficiency, diabetes insipidus, hyperthyroidism, hypothyroidism.

Hemic and Lymphatic: agranulocytosis, anemia (macrocytic, megaloblastic, microcytic, normocytic), aplastic anemia, hemolytic anemia, bleeding time increased, cyanosis, DIC, ecchymosis, eosinophilia, hypervolemia, leukopenia, lymphadenopathy, lymphangitis, marrow depression, pancytopenia, petechia, purpura, enlarged spleen, thrombocytopenia, thrombotic thrombocytopenic purpura.

Metabolic and Nutritional: albuminuria, BUN increased, creatine phosphokinase increased, edema, glucose tolerance decreased, hypercalcemia, hypercholesteremia, hyperglycemia, hyperkalemia, hypermagnesemia, hypernatremia, hyperuricemia, hypocalcemia, hypoglycemia, hypomagnesemia, hyponatremia, hypophosphatemia, peripheral edema, uremia.

Musculoskeletal: arthralgia, arthritis, bone necrosis, bone pain, leg cramps, myalgia, myasthenia, myopathy, osteomalacia, osteoporosis.

Nervous System: abnormal dreams, acute brain syndrome, agitation, akathisia, amnesia, anxiety, ataxia, brain edema, coma, confusion, convulsion, delirium, dementia, depersonalization, depression, diplopia, dizziness, encephalitis, encephalopathy, euphoria, Extrapyramidal Syndrome, grand mal convulsion, Guillain-Barré syndrome, hypertonia, hypesthesia, insomnia, intracranial hypertension, libido decreased, neuralgia, neuropathy, nystagmus, oculogyric crisis, paresthesia, psychosis, somnolence, suicidal ideation, tremor, vertigo.

Respiratory System: cough increased, dyspnea, epistaxis, hemoptysis, hypoxia, lung edema, pharyngitis, pleural effusion, pneumonia, respiratory disorder, respiratory distress syndrome, respiratory tract infection, rhinitis, sinusitis, voice alteration.

Skin and Appendages: alopecia, angioedema, contact dermatitis, discoid lupus erythematosis, eczema, erythema multiforme, exfoliative dermatitis, fixed drug eruption, furunculosis, herpes simplex, maculopapular rash, melanoma, melanosis, photosensitivity skin reaction, pruritus, pseudoporphyria, psoriasis, skin discoloration, skin disorder, skin dry, Stevens-Johnson syndrome, squamous cell carcinoma (including cutaneous SCC in situ, or Bowen's disease), sweating, toxic epidermal necrolysis, urticaria.

Special Senses: abnormality of accommodation, blepharitis, color blindness, conjunctivitis, corneal opacity, deafness, ear pain, eye pain, eye hemorrhage, dry eyes, hypoacusis, keratitis, keratoconjunctivitis, mydriasis, night blindness, optic atrophy, optic neuritis, otitis externa, papilledema, retinal hemorrhage, retinitis, scleritis, taste loss, taste perversion, tinnitus, uveitis, visual field defect.

Urogenital: anuria, blighted ovum, creatinine clearance decreased, dysmenorrhea, dysuria, epididymitis, glycosuria, hemorrhagic cystitis, hematuria, hydronephrosis, impotence, kidney pain, kidney tubular necrosis, metrorrhagia, nephritis, nephrosis, oliguria, scrotal edema, urinary incontinence, urinary retention, urinary tract infection, uterine hemorrhage, vaginal hemorrhage.

Clinical Laboratory Values in Adults

The overall incidence of transaminase increases >3× upper limit of normal (not necessarily comprising an adverse reaction) was 17.7% (268/1514) in adult subjects treated with VFEND for therapeutic use in pooled clinical trials. Increased incidence of liver function test abnormalities may be associated with higher plasma concentrations and/or doses. The majority of abnormal liver function tests either resolved during treatment without dose adjustment or resolved following dose adjustment, including discontinuation of therapy.

VFEND has been infrequently associated with cases of serious hepatic toxicity including cases of jaundice and rare cases of hepatitis and hepatic failure leading to death. Most of these patients had other serious underlying conditions.

Liver function tests should be evaluated at the start of and during the course of VFEND therapy. Patients who develop abnormal liver function tests during VFEND therapy should be monitored for the development of more severe hepatic injury. Patient management should include laboratory evaluation of hepatic function (particularly liver function tests and bilirubin). Discontinuation of VFEND must be considered if clinical signs and symptoms consistent with liver disease develop that may be attributable to VFEND [see Warnings and Precautions (5.1)].

Acute renal failure has been observed in severely ill patients undergoing treatment with VFEND. Patients being treated with VFEND are likely to be treated concomitantly with nephrotoxic medications and may have concurrent conditions that can result in decreased renal function. It is recommended that patients are monitored for the development of abnormal renal function. This should include laboratory evaluation of serum creatinine.

Tables 5 to 7 show the number of patients with hypokalemia and clinically significant changes in renal and liver function tests in three randomized, comparative multicenter studies. In study 305, patients with EC were randomized to either oral VFEND or oral fluconazole. In study 307/602, patients with definite or probable IA were randomized to either VFEND or amphotericin B therapy. In study 608, patients with candidemia were randomized to either VFEND or the regimen of amphotericin B followed by fluconazole.

Table 5: Protocol 305 – Patients with Esophageal Candidiasis Clinically Significant Laboratory Test Abnormalities
 | Criteria [Without regard to baseline value] | Voriconazole | Fluconazole
 |  | n/N (%) | n/N (%)
T. Bilirubin | >1.5× ULN | 8/185 (4.3) | 7/186 (3.8)
AST | >3.0× ULN | 38/187 (20.3) | 15/186 (8.1)
ALT | >3.0× ULN | 20/187 (10.7) | 12/186 (6.5)
Alkaline Phosphatase | >3.0× ULN | 19/187 (10.2) | 14/186 (7.5)
n = number of patients with a clinically significant abnormality while on study therapy
N = total number of patients with at least one observation of the given lab test while on study therapy
AST = Aspartate aminotransferase; ALT= alanine aminotransferase
ULN = upper limit of normal

Table 6: Protocol 307/602 – Primary Treatment of Invasive Aspergillosis Clinically Significant Laboratory Test Abnormalities
 | Criteria [Without regard to baseline value] | Voriconazole | Amphotericin B [Amphotericin B followed by other licensed antifungal therapy]
 |  | n/N (%) | n/N (%)
T. Bilirubin | >1.5× ULN | 35/180 (19.4) | 46/173 (26.6)
AST | >3.0× ULN | 21/180 (11.7) | 18/174 (10.3)
ALT | >3.0× ULN | 34/180 (18.9) | 40/173 (23.1)
Alkaline Phosphatase | >3.0× ULN | 29/181 (16.0) | 38/173 (22.0)
Creatinine | >1.3× ULN | 39/182 (21.4) | 102/177 (57.6)
Potassium | <0.9× LLN | 30/181 (16.6) | 70/178 (39.3)
n = number of patients with a clinically significant abnormality while on study therapy
N = total number of patients with at least one observation of the given lab test while on study therapy
AST = Aspartate aminotransferase; ALT = alanine aminotransferase
ULN = upper limit of normal
LLN = lower limit of normal

Table 7: Protocol 608 – Treatment of Candidemia Clinically Significant Laboratory Test Abnormalities
 | Criteria [Without regard to baseline value] | Voriconazole | Amphotericin B followed by Fluconazole
 |  | n/N (%) | n/N (%)
T. Bilirubin | >1.5× ULN | 50/261 (19.2) | 31/115 (27.0)
AST | >3.0× ULN | 40/261 (15.3) | 16/116 (13.8)
ALT | >3.0× ULN | 22/261 (8.4) | 15/116 (12.9)
Alkaline Phosphatase | >3.0× ULN | 59/261 (22.6) | 26/115 (22.6)
Creatinine | >1.3× ULN | 39/260 (15.0) | 32/118 (27.1)
Potassium | <0.9× LLN | 43/258 (16.7) | 35/118 (29.7)
n = number of patients with a clinically significant abnormality while on study therapy
N = total number of patients with at least one observation of the given lab test while on study therapy
AST = Aspartate aminotransferase; ALT = alanine aminotransferase
ULN = upper limit of normal
LLN = lower limit of normal

Clinical Trials Experience in Pediatric Patients

The safety of VFEND was investigated in 105 pediatric patients aged 2 to less than 18 years, including 52 pediatric patients less than 18 years of age who were enrolled in the adult therapeutic studies.

Serious Adverse Reactions and Adverse Reactions Leading to Discontinuation

In clinical studies, serious adverse reactions occurred in 46% (48/105) of VFEND treated pediatric patients. Treatment discontinuations due to adverse reactions occurred in 12 /105 (11%) of all patients. Hepatic adverse reactions (i.e. ALT increased; liver function test abnormal; jaundice) 6% (6/105) accounted for the majority of VFEND treatment discontinuations.

Most Common Adverse Reactions

The most common adverse reactions occurring in ≥5% of pediatric patients receiving VFEND in the pooled pediatric clinical trials are displayed by body system, in Table 8.

Table 8: Adverse Reactions Occurring in ≥5% of Pediatric Patients Receiving VFEND in the Pooled Pediatric Clinical Trials
Body System | Adverse Reaction | Pooled Pediatric Data [Reflects all adverse reactions and not treatment-related only.] N=105 n (%)
Blood and Lymphatic Systems Disorders | Thrombocytopenia | 10 (10)
Cardiac Disorders | Tachycardia | 7 (7)
Eye Disorders | Visual Disturbances [Pooled reports include such terms as: amaurosis (partial or total blindness without visible change in the eye); asthenopia (eye strain); chromatopsia (abnormally colored vision); color blindness; diplopia; photopsia; retinal disorder; vision blurred, visual acuity decreased, visual brightness; visual impairment. Several patients had more than one visual disturbance.] | 27 (26)
Eye Disorders | Photophobia | 6 (6)
Gastrointestinal Disorders | Vomiting | 21 (20)
Gastrointestinal Disorders | Nausea | 14 (13)
Gastrointestinal Disorders | Abdominal pain [Pooled reports include such terms as: abdominal pain and abdominal pain, upper.] | 13 (12)
Gastrointestinal Disorders | Diarrhea | 12 (11)
Gastrointestinal Disorders | Abdominal distention | 5 (5)
Gastrointestinal Disorders | Constipation | 5 (5)
General Disorders and Administration Site Conditions | Pyrexia | 25 (25)
General Disorders and Administration Site Conditions | Peripheral edema | 9 (9)
General Disorders and Administration Site Conditions | Mucosal inflammation | 6 (6)
Infections and Infestations | Upper respiratory tract infection | 5 (5)
Investigations | ALT abnormal [Pooled reports include such terms as: ALT abnormal and ALT increased.] | 9 (9)
Investigations | LFT abnormal | 6 (6)
Metabolism and Nutrition Disorders | Hypokalemia | 11 (11)
Metabolism and Nutrition Disorders | Hyperglycemia | 7 (7)
Metabolism and Nutrition Disorders | Hypocalcemia | 6 (6)
Metabolism and Nutrition Disorders | Hypophosphotemia | 6 (6)
Metabolism and Nutrition Disorders | Hypoalbuminemia | 5 (5)
Metabolism and Nutrition Disorders | Hypomagnesemia | 5 (5)
Nervous System Disorders | Headache | 10 (10)
Nervous System Disorders | Dizziness | 5 (5)
Psychiatric Disorders | Hallucinations [Pooled reports include such terms as: hallucination; hallucination, auditory; hallucination, visual. Several patients had both visual and auditory hallucinations.] | 5 (5)
Renal and Urinary Disorders | Renal impairment [Pooled reports include such terms as: renal failure and a single patient with renal impairment.] | 5 (5)
Respiratory Disorders | Epistaxis | 17 (16)
Respiratory Disorders | Cough | 10 (10)
Respiratory Disorders | Dyspnea | 6 (6)
Respiratory Disorders | Hemoptysis | 5 (5)
Skin and Subcutaneous Tissue Disorders | Rash [Pooled reports include such terms as: rash; rash generalized; rash macular; rash maculopapular; rash pruritic.] | 14 (13)
Vascular Disorders | Hypertension | 12 (11)
Vascular Disorders | Hypotension | 9 (9)
Abbreviations: ALT = alanine aminotransferase; LFT = liver function test

The following adverse reactions with incidence less than 5% were reported in 105 pediatric patients treated with VFEND:

Blood and Lymphatic System Disorders: anemia, leukopenia, pancytopenia

Cardiac Disorders: bradycardia, palpitations, supraventricular tachycardia

Eye Disorders: dry eye, keratitis

Ear and Labyrinth Disorders: tinnitus, vertigo

Gastrointestinal Disorders: abdominal tenderness, dyspepsia

General Disorders and Administration Site Conditions: asthenia, catheter site pain, chills, hypothermia, lethargy

Hepatobiliary Disorders: cholestasis, hyperbilirubinemia, jaundice

Immune System Disorders: hypersensitivity, urticaria

Infections and Infestations: conjunctivitis

Laboratory Investigations: AST increased, blood creatinine increased, gamma-glutamyl transferase increased

Metabolism and Nutrition Disorders: hypercalcemia, hypermagnesemia, hyperphosphatemia, hypoglycemia

Musculoskeletal and Connective Tissue Disorders: arthralgia, myalgia

Nervous System Disorders: ataxia, convulsion, dizziness, nystagmus, paresthesia, syncope

Psychiatric Disorders: affect lability, agitation, anxiety, depression, insomnia

Respiratory Disorders: bronchospasm, nasal congestion, respiratory failure, tachypnea

Skin and Subcutaneous Tissue Disorders: alopecia, dermatitis (allergic, contact, and exfoliative), pruritus

Vascular Disorders: flushing, phlebitis

Hepatic-Related Adverse Reactions in Pediatric Patients

The frequency of hepatic-related adverse reactions in pediatric patients exposed to VFEND in therapeutic studies was numerically higher than that of adults (28.6% compared to 24.1%, respectively). The higher frequency of hepatic adverse reactions in the pediatric population was mainly due to an increased frequency of liver enzyme elevations (21.9% in pediatric patients compared to 16.1% in adults), including transaminase elevations (ALT and AST combined) 7.6% in the pediatric patients compared to 5.1% in adults.

Clinical Laboratory Values in Pediatric Patients

The overall incidence of transaminase increases >3× upper limit of normal was 27.2% (28/103) in pediatric and 17.7% (268/1514) in adult patients treated with VFEND in pooled clinical trials. The majority of abnormal liver function tests either resolved on treatment with or without dose adjustment or after VFEND discontinuation.

A higher frequency of clinically significant liver laboratory abnormalities, irrespective of baseline laboratory values (>3× ULN ALT or AST), was consistently observed in the combined therapeutic pediatric population (15.5% AST and 22.5% ALT) when compared to adults (12.9% AST and 11.6% ALT). The incidence of bilirubin elevation was comparable between adult and pediatric patients. The incidence of hepatic abnormalities in pediatric patients is shown in Table 9.

Table 9: Incidence of Hepatic Abnormalities among Pediatric Subjects
 | Criteria | n/N (%)
Total bilirubin | >1.5× ULN | 19/102 (19)
AST | >3.0× ULN | 16/103 (16)
ALT | >3.0× ULN | 23/102 (23)
Alkaline Phosphatase | >3.0× ULN | 8/97 (8)
n = number of patients with a clinically significant abnormality while on study therapy
N = total number of patients with at least one observation of the given lab test while on study therapy
AST = Aspartate aminotransferase; ALT = alanine aminotransferase
ULN = upper limit of normal

6.2 Postmarketing Experience in Adult and Pediatric Patients

The following adverse reactions have been identified during post-approval use of VFEND. Because these reactions are reported voluntarily from a population of uncertain size, it is not always possible to reliably estimate their frequency or establish a causal relationship to drug exposure.

Dermatological Reactions

Increased risk of skin toxicity with concomitant use of methotrexate, a drug associated with UV reactivation, was observed in postmarketing reports [see Warnings and Precautions (5.6) and Adverse Reactions (6.1)].

Adults

Skeletal: fluorosis and periostitis have been reported during long-term voriconazole therapy [see Warnings and Precautions (5.12)].

Eye disorders: prolonged visual adverse reactions, including optic neuritis and papilledema [see Warnings and Precautions (5.4)].

Skin and Appendages: drug reaction with eosinophilia and systemic symptoms (DRESS) has been reported [see Warnings and Precautions (5.5) and Adverse Reactions (6.1)].

Endocrine disorders: adrenal insufficiency, Cushing's syndrome (when voriconazole has been used concomitantly with corticosteroids) [see Warnings and Precautions (5.8)].

Pediatric Patients

There have been postmarketing reports of pancreatitis in pediatric patients.

7 DRUG INTERACTIONS

Voriconazole is metabolized by cytochrome P450 isoenzymes, CYP2C19, CYP2C9, and CYP3A4. Therefore, inhibitors or inducers of these isoenzymes may increase or decrease voriconazole plasma concentrations, respectively. Voriconazole is a strong inhibitor of CYP3A4, and also inhibits CYP2C19 and CYP2C9. Therefore, voriconazole may increase the plasma concentrations of substances metabolized by these CYP450 isoenzymes.

Table 10 and Table 11 provide listings of clinically significant drug interactions, including contraindicated drugs [see Contraindications (4)]. Drugs listed in Table 10 and Table 11 are a guide and not considered a comprehensive list of all possible drugs and herbal products that are contraindicated or may interact with VFEND.

Table 10: Effect of Other Drugs on Voriconazole Pharmacokinetics [see Clinical Pharmacology (12.3)]

Drug/Drug Class (Mechanism of Interaction by the Drug) | Voriconazole Plasma Exposure (Cmax and AUCτ after 200 mg every 12 hours) | Prevention or Management Recommendations
Rifampin [Results based on in vivo clinical studies generally following repeat oral dosing with 200 mg every 12 hours voriconazole to healthy subjects] and Rifabutin (CYP450 Induction) | Significantly Reduced | Contraindicated
Efavirenz (400 mg every 24 hours) [Results based on in vivo clinical study following repeat oral dosing with 400 mg every 12 hours for 1 day, then 200 mg every 12 hours for at least 2 days voriconazole to healthy subjects] (CYP450 Induction) | Significantly Reduced | Contraindicated
Efavirenz (300 mg every 24 hours) (CYP450 Induction) | Slight Decrease in AUCτ | When voriconazole is concomitantly administered with efavirenz, voriconazole oral maintenance dose should be increased to 400 mg every 12 hours and efavirenz should be decreased to 300 mg every 24 hours.
High-dose Ritonavir (400 mg every 12 hours) (CYP450 Induction) | Significantly Reduced | Contraindicated
Low-dose Ritonavir (100 mg every 12 hours) (CYP450 Induction) | Reduced | Concomitant administration of voriconazole and low-dose ritonavir (100 mg every 12 hours) should be avoided, unless an assessment of the benefit/risk to the patient justifies the use of voriconazole.
Carbamazepine (CYP450 Induction) | Not Studied In Vivo or In Vitro, but Likely to Result in Significant Reduction | Contraindicated
Long Acting Barbiturates (e.g., phenobarbital, mephobarbital) (CYP450 Induction) | Not Studied In Vivo or In Vitro, but Likely to Result in Significant Reduction | Contraindicated
Phenytoin (CYP450 Induction) | Significantly Reduced | Increase voriconazole maintenance dose from 4 mg/kg to 5 mg/kg IV every 12 hours or from 200 mg to 400 mg orally every 12 hours (100 mg to 200 mg orally every 12 hours in patients weighing less than 40 kg).
Letermovir (CYP2C9/2C19 Induction) | Reduced | If concomitant administration of voriconazole with letermovir cannot be avoided, monitor for reduced effectiveness of voriconazole.
St. John's Wort (CYP450 inducer; P-gp inducer) | Significantly Reduced | Contraindicated
Oral Contraceptives containing ethinyl estradiol and norethindrone (CYP2C19 Inhibition) | Increased | Monitoring for adverse reactions and toxicity related to voriconazole is recommended for concomitant administration with oral contraceptives.
Fluconazole (CYP2C9, CYP2C19 and CYP3A4 Inhibition) | Significantly Increased | Avoid concomitant administration of voriconazole and fluconazole. Monitoring for adverse reactions and toxicity related to voriconazole is started within 24 hours after the last dose of fluconazole.
Other HIV Protease Inhibitors (CYP3A4 Inhibition) | In Vivo Studies Showed No Significant Effects of Indinavir on Voriconazole Exposure | No dosage adjustment in the voriconazole dosage needed for concomitant administration with indinavir.
 | In Vitro Studies Demonstrated Potential for Inhibition of Voriconazole Metabolism (Increased Plasma Exposure) | Frequent monitoring for adverse reactions and toxicity related to voriconazole for concomitant administration with other HIV protease inhibitors.
Other NNRTIs [Non-Nucleoside Reverse Transcriptase Inhibitors] (CYP3A4 Inhibition or CYP450 Induction) | In Vitro Studies Demonstrated Potential for Inhibition of Voriconazole Metabolism by Delavirdine and Other NNRTIs (Increased Plasma Exposure) | Frequent monitoring for adverse reactions and toxicity related to voriconazole.
 | A Voriconazole-Efavirenz Drug Interaction Study Demonstrated the Potential for the Metabolism of Voriconazole to be Induced by Efavirenz and Other NNRTIs (Decreased Plasma Exposure) | Careful assessment of voriconazole effectiveness.

Table 11: Effect of Voriconazole on Pharmacokinetics of Other Drugs [see Clinical Pharmacology (12.3)]

Drug/Drug Class (Mechanism of Interaction by Voriconazole) | Drug Plasma Exposure (Cmax and AUCτ) | Prevention or Management Recommendations
Sirolimus [Results based on in vivo clinical studies generally following repeat oral dosing with 200 mg BID voriconazole to healthy subjects] (CYP3A4 Inhibition) | Significantly Increased | Contraindicated
Rifabutin (CYP3A4 Inhibition) | Significantly Increased | Contraindicated
Efavirenz (400 mg every 24 hours) [Results based on in vivo clinical study following repeat oral dosing with 400 mg every 12 hours for 1 day, then 200 mg every 12 hours for at least 2 days voriconazole to healthy subjects] (CYP3A4 Inhibition) | Significantly Increased | Contraindicated
Efavirenz (300 mg every 24 hours) (CYP3A4 Inhibition) | Slight Increase in AUCτ | When voriconazole is concomitantly administered with efavirenz, voriconazole oral maintenance dose should be increased to 400 mg every 12 hours and efavirenz should be decreased to 300 mg every 24 hours.
High-dose Ritonavir (400 mg every 12 hours)(CYP3A4 Inhibition) | No Significant Effect of Voriconazole on Ritonavir Cmax or AUCτ | Contraindicated because of significant reduction of voriconazole Cmax and AUCτ.
Low-dose Ritonavir (100 mg every 12 hours) | Slight Decrease in Ritonavir Cmax and AUCτ | Concomitant administration of voriconazole and low-dose ritonavir (100 mg every 12 hours) should be avoided (due to the reduction in voriconazole Cmax and AUCτ) unless an assessment of the benefit/risk to the patient justifies the use of voriconazole.
Pimozide, Quinidine, Ivabradine (CYP3A4 Inhibition) | Not Studied In Vivo or In Vitro, but Drug Plasma Exposure Likely to be Increased | Contraindicated because of potential for QT prolongation and rare occurrence of torsade de pointes.
Ergot Alkaloids (CYP450 Inhibition) | Not Studied In Vivo or In Vitro, but Drug Plasma Exposure Likely to be Increased | Contraindicated
Naloxegol (CYP3A4 Inhibition) | Not Studied In Vivo or In Vitro, but Drug Plasma Exposure Likely to be Increased which may Increase the Risk of Adverse Reactions | Contraindicated
Tolvaptan (CYP3A4 Inhibition) | Although Not Studied Clinically, Voriconazole is Likely to Significantly Increase the Plasma Concentrations of Tolvaptan | Contraindicated
Lurasidone; (CYP3A4 Inhibition) | Not Studied In Vivo or In Vitro, but Voriconazole is Likely to Significantly Increase the Plasma Concentrations of Lurasidone | Contraindicated
Finerenone; (CYP3A4 Inhibition) | Not Studied In Vivo or In Vitro, but Voriconazole is Likely to Significantly Increase the Plasma Concentrations of Finerenone | Contraindicated
Eplerenone; (CYP3A4 Inhibition) | Not Studied In Vivo or In Vitro, but Voriconazole is Likely to Significantly Increase the Plasma Concentrations of Eplerenone | Contraindicated
Voclosporin; (CYP3A4 Inhibition) | Not Studied In Vivo or In Vitro, but Voriconazole is Likely to Significantly Increase the Plasma Concentrations of Voclosporin | Contraindicated
Venetoclax (CYP3A4 Inhibition) | Not Studied In Vivo or In Vitro, but Venetoclax Plasma Exposure Likely to be Significantly Increased | Concomitant administration of voriconazole is contraindicated at initiation and during the ramp-up phase in patients with chronic lymphocytic leukemia (CLL) or small lymphocytic lymphoma (SLL). Refer to the venetoclax labeling for safety monitoring and dose reduction in the steady daily dosing phase in CLL/SLL patients. For patients with acute myeloid leukemia (AML), dose reduction and safety monitoring are recommended across all dosing phases when concomitantly administered VFEND with venetoclax. Refer to the venetoclax prescribing information for dosing instructions.
Lemborexant (CYP3A4 Inhibition) | Not Studied In Vivo or In Vitro, but Drug Plasma Exposure Likely to be Increased | Avoid concomitant use of VFEND with lemborexant.
Glasdegib (CYP3A4 Inhibition) | Not Studied In Vivo or In Vitro, but Drug Plasma Exposure Likely to be Increased | Consider alternative therapies. If concomitant use cannot be avoided, monitor patients for increased risk of adverse reactions including QTc interval prolongation.
Tyrosine kinase inhibitors (including but not limited to axitinib, bosutinib, cabozantinib, ceritinib, cobimetinib, dabrafenib, dasatinib, nilotinib, sunitinib, ibrutinib, ribociclib) (CYP3A4 Inhibition) | Not Studied In Vivo or In Vitro, but Drug Plasma Exposure Likely to be Increased | Avoid concomitant use of VFEND. If concomitant use cannot be avoided, dose reduction of the tyrosine kinase inhibitor is recommended. Refer to the prescribing information for the relevant product.
Cyclosporine (CYP3A4 Inhibition) | AUCτ Significantly Increased; No Significant Effect on Cmax | When initiating therapy with VFEND in patients already receiving cyclosporine, reduce the cyclosporine dose to one-half of the starting dose and follow with frequent monitoring of cyclosporine blood levels. Increased cyclosporine levels have been associated with nephrotoxicity. When VFEND is discontinued, cyclosporine concentrations must be frequently monitored and the dose increased as necessary.
Methadone [Results based on in vivo clinical study following repeat oral dosing with 400 mg every 12 hours for 1 day, then 200 mg every 12 hours for 4 days voriconazole to subjects receiving a methadone maintenance dose (30–100 mg every 24 hours)] (CYP3A4 Inhibition) | Increased | Increased plasma concentrations of methadone have been associated with toxicity including QT prolongation. Frequent monitoring for adverse reactions and toxicity related to methadone is recommended when concomitantly administered with VFEND. Dose reduction of methadone may be needed.
Fentanyl (CYP3A4 Inhibition) | Increased | Reduction in the dose of fentanyl and other long-acting opiates metabolized by CYP3A4 should be considered when concomitantly administered with VFEND. Extended and frequent monitoring for opiate-associated adverse reactions may be necessary.
Alfentanil (CYP3A4 Inhibition) | Significantly Increased | An increase in the incidence of delayed and persistent alfentanil-associated nausea and vomiting were observed when concomitantly administered with VFEND. Reduction in the dose of alfentanil and other opiates metabolized by CYP3A4 (e.g., sufentanil) should be considered when concomitantly administered with VFEND. A longer period for monitoring respiratory and other opiate-associated adverse reactions may be necessary.
Oxycodone (CYP3A4 Inhibition) | Significantly Increased | Increased visual effects (heterophoria and miosis) of oxycodone were observed when concomitantly administered with VFEND. Reduction in the dose of oxycodone and other long-acting opiates metabolized by CYP3A4 should be considered when concomitantly administered with VFEND. Extended and frequent monitoring for opiate-associated adverse reactions may be necessary.
NSAIDs [Non-Steroidal Anti-Inflammatory Drug] including. ibuprofen and diclofenac (CYP2C9 Inhibition) | Increased | Frequent monitoring for adverse reactions and toxicity related to NSAIDs. Dose reduction of NSAIDs may be needed.
Tacrolimus (CYP3A4 Inhibition) | Significantly Increased | When initiating therapy with VFEND in patients already receiving tacrolimus, reduce the tacrolimus dose to one-third of the starting dose and follow with frequent monitoring of tacrolimus blood levels. Increased tacrolimus levels have been associated with nephrotoxicity. When VFEND is discontinued, tacrolimus concentrations must be frequently monitored and the dose increased as necessary.
Phenytoin (CYP2C9 Inhibition) | Significantly Increased | Frequent monitoring of phenytoin plasma concentrations and frequent monitoring of adverse effects related to phenytoin.
Oral Contraceptives containing ethinyl estradiol and norethindrone (CYP3A4 Inhibition) | Increased | Monitoring for adverse reactions related to oral contraceptives is recommended during concomitant administration.
Prednisolone and other corticosteroids (CYP3A4 Inhibition) | In Vivo Studies Showed No Significant Effects of VFEND on Prednisolone Exposure Not Studied In vitro or In vivo for Other Corticosteroids, but Drug Exposure Likely to be Increased | No dosage adjustment for prednisolone when concomitantly administered with VFEND [see Clinical Pharmacology (12.3)]. Monitor for potential adrenal dysfunction when VFEND is administered with other corticosteroids [see Warnings and Precautions (5.8)].
Warfarin (CYP2C9 Inhibition) | Prothrombin Time Significantly Increased | If patients receiving coumarin preparations are treated simultaneously with voriconazole, the prothrombin time or other suitable anticoagulation tests should be monitored at close intervals and the dosage of anticoagulants adjusted accordingly.
Other Oral Coumarin Anticoagulants (CYP2C9/3A4 Inhibition) | Not Studied In Vivo or In Vitro for other Oral Coumarin Anticoagulants, but Drug Plasma Exposure Likely to be Increased | If patients receiving coumarin preparations are treated simultaneously with voriconazole, the prothrombin time or other suitable anticoagulation tests should be monitored at close intervals and the dosage of anticoagulants adjusted accordingly.
Ivacaftor (CYP3A4 Inhibition) | Not Studied In Vivo or In Vitro, but Drug Plasma Exposure Likely to be Increased which may Increase the Risk of Adverse Reactions | Dose reduction of ivacaftor is recommended. Refer to the prescribing information for ivacaftor.
Eszopiclone (CYP3A4 Inhibition) | Not Studied In Vivo or In Vitro, but Drug Plasma Exposure Likely to be Increased which may Increase the Sedative Effect of Eszopiclone | Dose reduction of eszopiclone is recommended. Refer to the prescribing information for eszopiclone.
Mavacamten; (CYP2C19/3A4/2C9 Inhibition) | Not Studied In Vivo or In Vitro, but Mavacamten Drug Plasma Exposure Likely to be Increased which may Increase the Risk of Heart Failure | Refer to the prescribing information for mavacamten.
Omeprazole (CYP2C19/3A4 Inhibition) | Significantly Increased | When initiating therapy with VFEND in patients already receiving omeprazole doses of 40 mg or greater, reduce the omeprazole dose by one-half. The metabolism of other proton pump inhibitors that are CYP2C19 substrates may also be inhibited by voriconazole and may result in increased plasma concentrations of other proton pump inhibitors.
Other HIV Protease Inhibitors (CYP3A4 Inhibition) | In Vivo Studies Showed No Significant Effects on Indinavir Exposure | No dosage adjustment for indinavir when concomitantly administered with VFEND.
 | In Vitro Studies Demonstrated Potential for Voriconazole to Inhibit Metabolism (Increased Plasma Exposure) | Frequent monitoring for adverse reactions and toxicity related to other HIV protease inhibitors.
Other NNRTIs [Non-Nucleoside Reverse Transcriptase Inhibitors] (CYP3A4 Inhibition) | A Voriconazole-Efavirenz Drug Interaction Study Demonstrated the Potential for Voriconazole to Inhibit Metabolism of Other NNRTIs (Increased Plasma Exposure) | Frequent monitoring for adverse reactions and toxicity related to NNRTI.
Tretinoin (CYP3A4 Inhibition) | Although Not Studied, Voriconazole may Increase Tretinoin Concentrations and Increase the Risk of Adverse Reactions | Frequent monitoring for signs and symptoms of pseudotumor cerebri or hypercalcemia.
Midazolam (CYP3A4 Inhibition) | Significantly Increased | Increased plasma exposures may increase the risk of adverse reactions and toxicities related to benzodiazepines.
Other benzodiazepines including triazolam and alprazolam (CYP3A4 Inhibition) | In Vitro Studies Demonstrated Potential for Voriconazole to Inhibit Metabolism (Increased Plasma Exposure) | Refer to drug-specific labeling for details.
HMG-CoA Reductase Inhibitors (Statins) (CYP3A4 Inhibition) | In Vitro Studies Demonstrated Potential for Voriconazole to Inhibit Metabolism (Increased Plasma Exposure) | Frequent monitoring for adverse reactions and toxicity related to statins. Increased statin concentrations in plasma have been associated with rhabdomyolysis. Adjustment of the statin dosage may be needed.
Dihydropyridine Calcium Channel Blockers (CYP3A4 Inhibition) | In Vitro Studies Demonstrated Potential for Voriconazole to Inhibit Metabolism (Increased Plasma Exposure) | Frequent monitoring for adverse reactions and toxicity related to calcium channel blockers. Adjustment of calcium channel blocker dosage may be needed.
Sulfonylurea Oral Hypoglycemics (CYP2C9 Inhibition) | Not Studied In Vivo or In Vitro, but Drug Plasma Exposure Likely to be Increased | Frequent monitoring of blood glucose and for signs and symptoms of hypoglycemia. Adjustment of oral hypoglycemic drug dosage may be needed.
Vinca Alkaloids (CYP3A4 Inhibition) | Not Studied In Vivo or In Vitro, but Drug Plasma Exposure Likely to be Increased | Frequent monitoring for adverse reactions and toxicity (i.e., neurotoxicity) related to vinca alkaloids. Reserve azole antifungals, including voriconazole, for patients receiving a vinca alkaloid who have no alternative antifungal treatment options.
Everolimus (CYP3A4 Inhibition) | Not Studied In Vivo or In Vitro, but Drug Plasma Exposure Likely to be Increased | Concomitant administration of voriconazole and everolimus is not recommended.

8 USE IN SPECIFIC POPULATIONS

8.1 Pregnancy

Risk Summary

Voriconazole can cause fetal harm when administered to a pregnant woman. There are no available data on the use of VFEND in pregnant women. In animal reproduction studies, oral voriconazole was associated with fetal malformations in rats and fetal toxicity in rabbits. Cleft palates and hydronephrosis/hydroureter were observed in rat pups exposed to voriconazole during organogenesis at and above 10 mg/kg (0.3 times the RMD of 200 mg every 12 hours based on body surface area comparisons). In rabbits, embryomortality, reduced fetal weight and increased incidence of skeletal variations, cervical ribs and extrasternal ossification sites were observed in pups when pregnant rabbits were orally dosed at 100 mg/kg (6 times the RMD based on body surface area comparisons) during organogenesis. Rats exposed to voriconazole from implantation to weaning experienced increased gestational length and dystocia, which were associated with increased perinatal pup mortality at the 10 mg/kg dose [see Data]. If this drug is used during pregnancy, or if the patient becomes pregnant while taking this drug, inform the patient of the potential hazard to the fetus [see Warnings and Precautions (5.9)].

The background risk of major birth defects and miscarriage for the indicated populations is unknown. In the U.S. general population, the estimated background risk of major birth defects and miscarriage in clinically recognized pregnancies is 2–4% and 15–20% respectively.

Data

Animal Data

Voriconazole was administered orally to pregnant rats during organogenesis (gestation days 6–17) at 10, 30, and 60 mg/kg/day..Voriconazole was associated with increased incidences of the malformations hydroureter and hydronephrosis at 10 mg/kg/day or greater, approximately 0.3 times the recommended human dose (RMD) based on body surface area comparisons, and cleft palate at 60 mg/kg, approximately 2 times the RMD based on body surface area comparisons. Reduced ossification of sacral and caudal vertebrae, skull, pubic, and hyoid bone, supernumerary ribs, anomalies of the sternebrae, and dilatation of the ureter/renal pelvis were also observed at doses of 10 mg/kg or greater. There was no evidence of maternal toxicity at any dose.

Voriconazole was administered orally to pregnant rabbits during the period of organogenesis (gestation days 7–19) at 10, 40, and 100 mg/kg/day. Voriconazole was associated with increased post-implantation loss and decreased fetal body weight, in association with maternal toxicity (decreased body weight gain and food consumption) at 100 mg/kg/day (6 times the RMD based on body surface area comparisons). Fetal skeletal variations (increases in the incidence of cervical rib and extra sternebral ossification sites) were observed at 100 mg/kg/day.

In a peri- and postnatal toxicity study in rats, voriconazole was administered orally to female rats from implantation through the end of lactation at 1, 3, and 10 mg/kg/day. Voriconazole prolonged the duration of gestation and labor and produced dystocia with related increases in maternal mortality and decreases in perinatal survival of F1 pups at 10 mg/kg/day, approximately 0.3 times the RMD.

8.2 Lactation

Risk Summary

No data are available regarding the presence of voriconazole in human milk, the effects of voriconazole on the breastfed infant, or the effects on milk production. The developmental and health benefits of breastfeeding should be considered along with the mother's clinical need for VFEND and any potential adverse effects on the breastfed child from VFEND or from the underlying maternal condition.

8.3 Females and Males of Reproductive Potential

Contraception

Advise females of reproductive potential to use effective contraception during treatment with VFEND. The coadministration of voriconazole with the oral contraceptive, Ortho-Novum® (35 mcg ethinyl estradiol and 1 mg norethindrone), results in an interaction between these two drugs, but is unlikely to reduce the contraceptive effect. Monitoring for adverse reactions associated with oral contraceptives and voriconazole is recommended [see Drug Interactions (7) and Clinical Pharmacology (12.3)].

8.4 Pediatric Use

The safety and effectiveness of VFEND have been established in pediatric patients 2 years of age and older based on evidence from adequate and well-controlled studies in adult and pediatric patients and additional pediatric pharmacokinetic and safety data. A total of 105 pediatric patients aged 2 to less than 12 [N=26] and aged 12 to less than 18 [N=79] from two, non-comparative Phase 3 pediatric studies and eight adult therapeutic trials provided safety information for VFEND use in the pediatric population [see Adverse Reactions (6.1), Clinical Pharmacology (12.3), and Clinical Studies (14)].

Safety and effectiveness in pediatric patients below the age of 2 years has not been established. Therefore, VFEND is not recommended for pediatric patients less than 2 years of age.

A higher frequency of liver enzyme elevations was observed in the pediatric patients [see Dosage and Administration (2.5), Warnings and Precautions (5.1), and Adverse Reactions (6.1)].

The frequency of phototoxicity reactions is higher in the pediatric population. Squamous cell carcinoma has been reported in patients who experience photosensitivity reactions. Stringent measures for photoprotection are warranted. Sun avoidance and dermatologic follow-up are recommended in pediatric patients experiencing photoaging injuries, such as lentigines or ephelides, even after treatment discontinuation [see Warnings and Precautions (5.6)].

VFEND has not been studied in pediatric patients with hepatic or renal impairment [see Dosage and Administration (2.5, 2.6)]. Hepatic function and serum creatinine levels should be closely monitored in pediatric patients [see Dosage and Administration (2.6) and Warnings and Precautions (5.1, 5.10)].

8.5 Geriatric Use

In multiple dose therapeutic trials of voriconazole, 9.2% of patients were ≥65 years of age and 1.8% of patients were ≥75 years of age. In a study in healthy subjects, the systemic exposure (AUC) and peak plasma concentrations (Cmax) were increased in elderly males compared to young males. Pharmacokinetic data obtained from 552 patients from 10 voriconazole therapeutic trials showed that voriconazole plasma concentrations in the elderly patients were approximately 80% to 90% higher than those in younger patients after either IV or oral administration. However, the overall safety profile of the elderly patients was similar to that of the young so no dosage adjustment is recommended [see Clinical Pharmacology (12.3)].

10 OVERDOSAGE

In clinical trials, there were three cases of accidental overdose. All occurred in pediatric patients who received up to five times the recommended intravenous dose of voriconazole. A single adverse reaction of photophobia of 10 minutes duration was reported.

There is no known antidote to voriconazole.

Voriconazole is hemodialyzed with clearance of 121 mL/min. The intravenous vehicle, SBECD, is hemodialyzed with clearance of 55 mL/min. In an overdose, hemodialysis may assist in the removal of voriconazole and SBECD from the body.

11 DESCRIPTION

VFEND (voriconazole), an azole antifungal agent is available as a lyophilized powder for solution for intravenous infusion, film-coated tablets for oral administration, and as a powder for oral suspension. The structural formula is:

Voriconazole is designated chemically as (2R,3S)-2-(2, 4-difluorophenyl)-3-(5-fluoro-4-pyrimidinyl)-1-(1H-1,2,4-triazol-1-yl)-2-butanol with an empirical formula of C16H14F3N5O and a molecular weight of 349.3.

Voriconazole drug substance is a white to light-colored powder.

VFEND I.V. is a white lyophilized powder containing nominally 200 mg voriconazole and 3200 mg sulfobutyl ether beta-cyclodextrin sodium in a 30 mL Type I clear glass vial.

VFEND I.V. is intended for administration by intravenous infusion. It is a single-dose, unpreserved product. Vials containing 200 mg lyophilized voriconazole are intended for reconstitution with Water for Injection to produce a solution containing 10 mg/mL VFEND and 160 mg/mL of sulfobutyl ether beta-cyclodextrin sodium. The resultant solution is further diluted prior to administration as an intravenous infusion [see Dosage and Administration (2)].

VFEND Tablets contain 50 mg or 200 mg of voriconazole. The inactive ingredients include croscarmellose sodium, lactose monohydrate, magnesium stearate, povidone, pregelatinized starch, and a coating containing hypromellose, lactose monohydrate, titanium dioxide, and triacetin.

VFEND for Oral Suspension is a white to off-white powder providing a white to off-white orange-flavored suspension when reconstituted. Bottles containing 45 grams powder for oral suspension, which contain 3 g of voriconazole, are intended for reconstitution with water to produce a suspension containing 40 mg/mL voriconazole. The inactive ingredients include anhydrous citric acid, colloidal silicon dioxide, natural orange flavor, sodium benzoate, sodium citrate dihydrate, sucrose, titanium dioxide, and xanthan gum.

12 CLINICAL PHARMACOLOGY

12.1 Mechanism of Action

Voriconazole is an antifungal drug [see Microbiology (12.4)].

12.2 Pharmacodynamics

Exposure-Response Relationship for Efficacy and Safety

In 10 clinical trials (N=1121), the median values for the average and maximum voriconazole plasma concentrations in individual patients across these studies was 2.51 µg/mL (inter-quartile range 1.21 to 4.44 µg/mL) and 3.79 µg/mL (inter-quartile range 2.06 to 6.31 µg/mL), respectively. A pharmacokinetic-pharmacodynamic analysis of patient data from 6 of these 10 clinical trials (N=280) could not detect a positive association between mean, maximum or minimum plasma voriconazole concentration and efficacy. However, pharmacokinetic/pharmacodynamic analyses of the data from all 10 clinical trials identified positive associations between plasma voriconazole concentrations and rate of both liver function test abnormalities and visual disturbances [see Adverse Reactions (6)].

Cardiac Electrophysiology

A placebo-controlled, randomized, crossover study to evaluate the effect on the QT interval of healthy male and female subjects was conducted with three single oral doses of voriconazole and ketoconazole. Serial ECGs and plasma samples were obtained at specified intervals over a 24-hour post dose observation period. The placebo-adjusted mean maximum increases in QTc from baseline after 800, 1200, and 1600 mg of voriconazole and after ketoconazole 800 mg were all <10 msec. Females exhibited a greater increase in QTc than males, although all mean changes were <10 msec. Age was not found to affect the magnitude of increase in QTc. No subject in any group had an increase in QTc of ≥60 msec from baseline. No subject experienced an interval exceeding the potentially clinically relevant threshold of 500 msec. However, the QT effect of voriconazole combined with drugs known to prolong the QT interval is unknown [see Contraindications (4) and Drug Interactions (7)].

12.3 Pharmacokinetics

The pharmacokinetics of voriconazole have been characterized in healthy subjects, special populations and patients.

The pharmacokinetics of voriconazole are non-linear due to saturation of its metabolism. The interindividual variability of voriconazole pharmacokinetics is high. Greater than proportional increase in exposure is observed with increasing dose. It is estimated that, on average, increasing the oral dose from 200 mg every 12 hours to 300 mg every 12 hours leads to an approximately 2.5-fold increase in exposure (AUCτ); similarly, increasing the intravenous dose from 3 mg/kg every 12 hours to 4 mg/kg every 12 hours produces an approximately 2.5-fold increase in exposure (Table 12).

Table 12: Geometric Mean (%CV) Plasma Voriconazole Pharmacokinetic Parameters in Adults Receiving Different Dosing Regimens
 | 6 mg/kg IV (loading dose) | 3 mg/kg IV every 12 hours | 4 mg/kg IV every 12 hours | 400 mg Oral (loading dose) | 200 mg Oral every 12 hours | 300 mg Oral every 12 hours
N | 35 | 23 | 40 | 17 | 48 | 16
AUC12 (μg∙h/mL) | 13.9 (32) | 13.7 (53) | 33.9 (54) | 9.31 (38) | 12.4 (78) | 34.0 (53)
Cmax (μg/mL) | 3.13 (20) | 3.03 (25) | 4.77 (36) | 2.30 (19) | 2.31 (48) | 4.74 (35)
Cmin (μg/mL) | -- | 0.46 (97) | 1.73 (74) | -- | 0.46 (120) | 1.63 (79)
Note: Parameters were estimated based on non-compartmental analysis from 5 pharmacokinetic studies.
AUC12 = area under the curve over 12 hour dosing interval, Cmax = maximum plasma concentration, Cmin = minimum plasma concentration. CV = coefficient of variation

When the recommended intravenous loading dose regimen is administered to healthy subjects, plasma concentrations close to steady state are achieved within the first 24 hours of dosing (e.g., 6 mg/kg IV every 12 hours on day 1 followed by 3 mg/kg IV every 12 hours). Without the loading dose, accumulation occurs during twice daily multiple dosing with steady state plasma voriconazole concentrations being achieved by day 6 in the majority of subjects.

Absorption

The pharmacokinetic properties of voriconazole are similar following administration by the intravenous and oral routes. Based on a population pharmacokinetic analysis of pooled data in healthy subjects (N=207), the oral bioavailability of voriconazole is estimated to be 96% (CV 13%). Bioequivalence was established between the 200 mg tablet and the 40 mg/mL oral suspension when administered as a 400 mg every 12 hours loading dose followed by a 200 mg every 12 hours maintenance dose.

Maximum plasma concentrations (Cmax) are achieved 1–2 hours after dosing. When multiple doses of voriconazole are administered with high-fat meals, the mean Cmax and AUCτ are reduced by 34% and 24%, respectively when administered as a tablet and by 58% and 37% respectively when administered as the oral suspension [see Dosage and Administration (2)].

In healthy subjects, the absorption of voriconazole is not affected by coadministration of oral ranitidine, cimetidine, or omeprazole, drugs that are known to increase gastric pH.

Distribution

The volume of distribution at steady state for voriconazole is estimated to be 4.6 L/kg, suggesting extensive distribution into tissues. Plasma protein binding is estimated to be 58% and was shown to be independent of plasma concentrations achieved following single and multiple oral doses of 200 mg or 300 mg (approximate range: 0.9–15 µg/mL). Varying degrees of hepatic and renal impairment do not affect the protein binding of voriconazole.

Elimination

Metabolism

In vitro studies showed that voriconazole is metabolized by the human hepatic cytochrome P450 enzymes, CYP2C19, CYP2C9 and CYP3A4 [see Drug Interactions (7)].

In vivo studies indicated that CYP2C19 is significantly involved in the metabolism of voriconazole. This enzyme exhibits genetic polymorphism [see Clinical Pharmacology (12.5)].

The major metabolite of voriconazole is the N-oxide, which accounts for 72% of the circulating radiolabelled metabolites in plasma. Since this metabolite has minimal antifungal activity, it does not contribute to the overall efficacy of voriconazole.

Excretion

Voriconazole is eliminated via hepatic metabolism with less than 2% of the dose excreted unchanged in the urine. After administration of a single radiolabelled dose of either oral or IV voriconazole, preceded by multiple oral or IV dosing, approximately 80% to 83% of the radioactivity is recovered in the urine. The majority (>94%) of the total radioactivity is excreted in the first 96 hours after both oral and intravenous dosing.

As a result of non-linear pharmacokinetics, the terminal half-life of voriconazole is dose dependent and therefore not useful in predicting the accumulation or elimination of voriconazole.

Specific Populations

Male and Female Patients

In a multiple oral dose study, the mean Cmax and AUCτ for healthy young females were 83% and 113% higher, respectively, than in healthy young males (18–45 years), after tablet dosing. In the same study, no significant differences in the mean Cmax and AUCτ were observed between healthy elderly males and healthy elderly females (>65 years). In a similar study, after dosing with the oral suspension, the mean AUC for healthy young females was 45% higher than in healthy young males whereas the mean Cmax was comparable between genders. The steady state trough voriconazole concentrations (Cmin) seen in females were 100% and 91% higher than in males receiving the tablet and the oral suspension, respectively.

In the clinical program, no dosage adjustment was made on the basis of gender. The safety profile and plasma concentrations observed in male and female subjects were similar. Therefore, no dosage adjustment based on gender is necessary.

Geriatric Patients

In an oral multiple dose study the mean Cmax and AUCτ in healthy elderly males (≥65 years) were 61% and 86% higher, respectively, than in young males (18–45 years). No significant differences in the mean Cmax and AUCτ were observed between healthy elderly females (≥65 years) and healthy young females (18–45 years).

In the clinical program, no dosage adjustment was made on the basis of age. An analysis of pharmacokinetic data obtained from 552 patients from 10 voriconazole clinical trials showed that the median voriconazole plasma concentrations in the elderly patients (>65 years) were approximately 80% to 90% higher than those in the younger patients (≤65 years) after either IV or oral administration. However, the safety profile of voriconazole in young and elderly subjects was similar and, therefore, no dosage adjustment is necessary for the elderly [see Use in Special Populations (8.5)].

Pediatric Patients

The recommended doses in pediatric patients were based on a population pharmacokinetic analysis of data obtained from 112 immunocompromised pediatric patients aged 2 to less than 12 years and 26 immunocompromised pediatric patients aged 12 to less than 17 years.

A comparison of the pediatric and adult population pharmacokinetic data indicated that the predicted total exposure (AUC12) in pediatric patients aged 2 to less than 12 years following administration of a 9 mg/kg intravenous loading dose was comparable to that in adults following a 6 mg/kg intravenous loading dose. The predicted total exposures in pediatric patients aged 2 to less than 12 years following intravenous maintenance doses of 4 and 8 mg/kg twice daily were comparable to those in adults following 3 and 4 mg/kg IV twice daily, respectively.

The predicted total exposure in pediatric patients aged 2 to less than 12 years following an oral maintenance dose of 9 mg/kg (maximum of 350 mg) twice daily was comparable to that in adults following 200 mg oral twice daily. An 8 mg/kg intravenous dose will provide voriconazole exposure approximately 2-fold higher than a 9 mg/kg oral dose in pediatric patients aged 2 to less than 12 years.

Voriconazole exposures in the majority of pediatric patients aged 12 to less than 17 years were comparable to those in adults receiving the same dosing regimens. However, lower voriconazole exposure was observed in some pediatric patients aged 12 to less than 17 years with low body weight compared to adults [see Dosage and Administration (2.4)].

Limited voriconazole trough plasma samples were collected in pediatric patients aged 2 to less than 18 years with IA or invasive candidiasis including candidemia, and EC in two prospective, open-label, non-comparative, multicenter clinical studies. In eleven pediatric patients aged 2 to less than 12 years and aged 12 to 14 years, with body weight less than 50 kg, who received 9 mg/kg intravenously every 12 hours as a loading dose on the first day of treatment, followed by 8 mg/kg every 12 hours as an intravenous maintenance dose, or 9 mg/kg every 12 hours as an oral maintenance dose, the mean trough concentration of voriconazole was 3.6 mcg/mL (range 0.3 to 10.7 mcg/mL). In four pediatric patients aged 2 to less than 12 years and aged 12 to 14 years, with body weight less than 50 kg, who received 4 mg/kg intravenously every 12 hours, the mean trough concentration of voriconazole was 0.9 mcg/mL (range 0.3 to 1.6 mcg/mL) [see Clinical Studies (14.5)].

Patients with Hepatic Impairment

After a single oral dose (200 mg) of voriconazole in 8 patients with mild (Child-Pugh Class A) and 4 patients with moderate (Child-Pugh Class B) hepatic impairment, the mean systemic exposure (AUC) was 3.2-fold higher than in age and weight matched controls with normal hepatic function. There was no difference in mean peak plasma concentrations (Cmax) between the groups. When only the patients with mild (Child-Pugh Class A) hepatic impairment were compared to controls, there was still a 2.3-fold increase in the mean AUC in the group with hepatic impairment compared to controls.

In an oral multiple dose study, AUCτ was similar in 6 subjects with moderate hepatic impairment (Child-Pugh Class B) given a lower maintenance dose of 100 mg twice daily compared to 6 subjects with normal hepatic function given the standard 200 mg twice daily maintenance dose. The mean peak plasma concentrations (Cmax) were 20% lower in the hepatically impaired group. No pharmacokinetic data are available for patients with severe hepatic cirrhosis (Child-Pugh Class C) [see Dosage and Administration (2.5)].

Patients with Renal Impairment

In a single oral dose (200 mg) study in 24 subjects with normal renal function and mild to severe renal impairment, systemic exposure (AUC) and peak plasma concentration (Cmax) of voriconazole were not significantly affected by renal impairment. Therefore, no adjustment is necessary for oral dosing in patients with mild to severe renal impairment.

In a multiple dose study of IV voriconazole (6 mg/kg IV loading dose × 2, then 3 mg/kg IV × 5.5 days) in 7 patients with moderate renal dysfunction (creatinine clearance 30–50 mL/min), the systemic exposure (AUC) and peak plasma concentrations (Cmax) were not significantly different from those in 6 subjects with normal renal function.

However, in patients with moderate renal dysfunction (creatinine clearance 30–50 mL/min), accumulation of the intravenous vehicle, SBECD, occurs. The mean systemic exposure (AUC) and peak plasma concentrations (Cmax) of SBECD were increased 4-fold and almost 50%, respectively, in the moderately impaired group compared to the normal control group.

A pharmacokinetic study in subjects with renal failure undergoing hemodialysis showed that voriconazole is dialyzed with clearance of 121 mL/min. The intravenous vehicle, SBECD, is hemodialyzed with clearance of 55 mL/min. A 4-hour hemodialysis session does not remove a sufficient amount of voriconazole to warrant dose adjustment [see Dosage and Administration (2.6)].

Patients at Risk of Aspergillosis

The observed voriconazole pharmacokinetics in patients at risk of aspergillosis (mainly patients with malignant neoplasms of lymphatic or hematopoietic tissue) were similar to healthy subjects.

Drug Interaction Studies

Effects of Other Drugs on Voriconazole

Voriconazole is metabolized by the human hepatic cytochrome P450 enzymes CYP2C19, CYP2C9, and CYP3A4. Results of in vitro metabolism studies indicate that the affinity of voriconazole is highest for CYP2C19, followed by CYP2C9, and is appreciably lower for CYP3A4. Inhibitors or inducers of these three enzymes may increase or decrease voriconazole systemic exposure (plasma concentrations), respectively.

The systemic exposure to voriconazole is significantly reduced by the concomitant administration of the following agents and their use is contraindicated:

Rifampin (potent CYP450 inducer)–Rifampin (600 mg once daily) decreased the steady state Cmax and AUCτ of voriconazole (200 mg every 12 hours × 7 days) by an average of 93% and 96%, respectively, in healthy subjects. Doubling the dose of voriconazole to 400 mg every 12 hours does not restore adequate exposure to voriconazole during coadministration with rifampin [see Contraindications (4)].

Ritonavir (potent CYP450 inducer; CYP3A4 inhibitor and substrate)–The effect of the coadministration of voriconazole and ritonavir (400 mg and 100 mg) was investigated in two separate studies. High-dose ritonavir (400 mg every 12 hours for 9 days) decreased the steady state Cmax and AUCτ of oral voriconazole (400 mg every 12 hours for 1 day, then 200 mg every 12 hours for 8 days) by an average of 66% and 82%, respectively, in healthy subjects. Low-dose ritonavir (100 mg every 12 hours for 9 days) decreased the steady state Cmax and AUCτ of oral voriconazole (400 mg every 12 hours for 1 day, then 200 mg every 12 hours for 8 days) by an average of 24% and 39%, respectively, in healthy subjects. Although repeat oral administration of voriconazole did not have a significant effect on steady state Cmax and AUCτ of high-dose ritonavir in healthy subjects, steady state Cmax and AUCτ of low-dose ritonavir decreased slightly by 24% and 14% respectively, when administered concomitantly with oral voriconazole in healthy subjects [see Contraindications (4)].

St. John's Wort (CYP450 inducer; P-gp inducer)–In an independent published study in healthy volunteers who were given multiple oral doses of St. John's Wort (300 mg LI 160 extract three times daily for 15 days) followed by a single 400 mg oral dose of voriconazole, a 59% decrease in mean voriconazole AUC0–∞ was observed. In contrast, coadministration of single oral doses of St. John's Wort and voriconazole had no appreciable effect on voriconazole AUC0–∞. Long-term use of St. John's Wort could lead to reduced voriconazole exposure [see Contraindications (4)].

Significant drug interactions that may require voriconazole dosage adjustment, or frequent monitoring of voriconazole-related adverse reactions/toxicity:

Fluconazole (CYP2C9, CYP2C19 and CYP3A4 inhibitor): Concurrent administration of oral voriconazole (400 mg every 12 hours for 1 day, then 200 mg every 12 hours for 2.5 days) and oral fluconazole (400 mg on day 1, then 200 mg every 24 hours for 4 days) to 6 healthy male subjects resulted in an increase in Cmax and AUCτ of voriconazole by an average of 57% (90% CI: 20%, 107%) and 79% (90% CI: 40%, 128%), respectively. In a follow-on clinical study involving 8 healthy male subjects, reduced dosing and/or frequency of voriconazole and fluconazole did not eliminate or diminish this effect [see Drug Interactions (7)].

Letermovir (CYP2C9/2C19 inducer)–Coadministration of oral letermovir with oral voriconazole decreased the steady state Cmax and AUC0–12 of voriconazole by an average of 39% and 44%, respectively [see Drug Interactions (7)].

Minor or no significant pharmacokinetic interactions that do not require dosage adjustment:

Cimetidine (non-specific CYP450 inhibitor and increases gastric pH)–Cimetidine (400 mg every 12 hours × 8 days) increased voriconazole steady state Cmax and AUCτ by an average of 18% (90% CI: 6%, 32%) and 23% (90% CI: 13%, 33%), respectively, following oral doses of 200 mg every 12 hours × 7 days to healthy subjects.

Ranitidine (increases gastric pH)–Ranitidine (150 mg every 12 hours) had no significant effect on voriconazole Cmax and AUCτ following oral doses of 200 mg every 12 hours × 7 days to healthy subjects.

Macrolide antibiotics–Coadministration of erythromycin (CYP3A4 inhibitor; 1 gram every 12 hours for 7 days) or azithromycin (500 mg every 24 hours for 3 days) with voriconazole 200 mg every 12 hours for 14 days had no significant effect on voriconazole steady state Cmax and AUCτ in healthy subjects. The effects of voriconazole on the pharmacokinetics of either erythromycin or azithromycin are not known.

Effects of Voriconazole on Other Drugs

In vitro studies with human hepatic microsomes show that voriconazole inhibits the metabolic activity of the cytochrome P450 enzymes CYP2C19, CYP2C9, and CYP3A4. In these studies, the inhibition potency of voriconazole for CYP3A4 metabolic activity was significantly less than that of two other azoles, ketoconazole and itraconazole. In vitro studies also show that the major metabolite of voriconazole, voriconazole N-oxide, inhibits the metabolic activity of CYP2C9 and CYP3A4 to a greater extent than that of CYP2C19. Therefore, there is potential for voriconazole and its major metabolite to increase the systemic exposure (plasma concentrations) of other drugs metabolized by these CYP450 enzymes.

The systemic exposure of the following drug is significantly increased by coadministration of voriconazole and their use is contraindicated:

Sirolimus (CYP3A4 substrate)–Repeat dose administration of oral voriconazole (400 mg every 12 hours for 1 day, then 200 mg every 12 hours for 8 days) increased the Cmax and AUC of sirolimus (2 mg single dose) an average of 7-fold (90% CI: 5.7, 7.5) and 11-fold (90% CI: 9.9, 12.6), respectively, in healthy male subjects [see Contraindications (4)].

Coadministration of voriconazole with the following agents results in increased exposure to these drugs. Therefore, careful monitoring and/or dosage adjustment of these drugs is needed:

Alfentanil (CYP3A4 substrate)–Coadministration of multiple doses of oral voriconazole (400 mg every 12 hours on day 1, 200 mg every 12 hours on day 2) with a single 20 mcg/kg intravenous dose of alfentanil with concomitant naloxone resulted in a 6-fold increase in mean alfentanil AUC0–∞ and a 4-fold prolongation of mean alfentanil elimination half-life, compared to when alfentanil was given alone [see Drug Interactions (7)].

Fentanyl (CYP3A4 substrate): In an independent published study, concomitant use of voriconazole (400 mg every 12 hours on Day 1, then 200 mg every 12 hours on Day 2) with a single intravenous dose of fentanyl (5 µg/kg) resulted in an increase in the mean AUC0–∞ of fentanyl by 1.4-fold (range 0.81- to 2.04-fold) [see Drug Interactions (7)].

Oxycodone (CYP3A4 substrate): In an independent published study, coadministration of multiple doses of oral voriconazole (400 mg every 12 hours, on Day 1 followed by five doses of 200 mg every 12 hours on Days 2 to 4) with a single 10 mg oral dose of oxycodone on Day 3 resulted in an increase in the mean Cmax and AUC0–∞ of oxycodone by 1.7-fold (range 1.4- to 2.2-fold) and 3.6-fold (range 2.7- to 5.6-fold), respectively. The mean elimination half-life of oxycodone was also increased by 2.0-fold (range 1.4- to 2.5-fold) [see Drug Interactions (7)].

Cyclosporine (CYP3A4 substrate)–In stable renal transplant recipients receiving chronic cyclosporine therapy, concomitant administration of oral voriconazole (200 mg every 12 hours for 8 days) increased cyclosporine Cmax and AUCτ an average of 1.1 times (90% CI: 0.9, 1.41) and 1.7 times (90% CI: 1.5, 2.0), respectively, as compared to when cyclosporine was administered without voriconazole [see Drug Interactions (7)].

Methadone (CYP3A4, CYP2C19, CYP2C9 substrate)–Repeat dose administration of oral voriconazole (400 mg every 12 hours for 1 day, then 200 mg every 12 hours for 4 days) increased the Cmax and AUCτ of pharmacologically active Rmethadone by 31% (90% CI: 22%, 40%) and 47% (90% CI: 38%, 57%), respectively, in subjects receiving a methadone maintenance dose (30–100 mg every 24 hours). The Cmax and AUC of (S)-methadone increased by 65% (90% CI: 53%, 79%) and 103% (90% CI: 85%, 124%), respectively [see Drug Interactions (7)].

Tacrolimus (CYP3A4 substrate)–Repeat oral dose administration of voriconazole (400 mg every 12 hours × 1 day, then 200 mg every 12 hours × 6 days) increased tacrolimus (0.1 mg/kg single dose) Cmax and AUCτ in healthy subjects by an average of 2-fold (90% CI: 1.9, 2.5) and 3-fold (90% CI: 2.7, 3.8), respectively [see Drug Interactions (7)].

Warfarin (CYP2C9 substrate)–Coadministration of voriconazole (300 mg every 12 hours × 12 days) with warfarin (30 mg single dose) significantly increased maximum prothrombin time by approximately 2 times that of placebo in healthy subjects [see Drug Interactions (7)].

Non-Steroidal Anti-Inflammatory Drugs (NSAIDs; CYP2C9 substrates): In two independent published studies, single doses of ibuprofen (400 mg) and diclofenac (50 mg) were coadministered with the last dose of voriconazole (400 mg every 12 hours on Day 1, followed by 200 mg every 12 hours on Day 2). Voriconazole increased the mean Cmax and AUC of the pharmacologically active isomer, S (+)-ibuprofen by 20% and 100%, respectively. Voriconazole increased the mean Cmax and AUC of diclofenac by 114% and 78%, respectively [see Drug Interactions (7)].

No significant pharmacokinetic interactions were observed when voriconazole was coadministered with the following agents. Therefore, no dosage adjustment for these agents is recommended:

Prednisolone (CYP3A4 substrate)–Voriconazole (200 mg every 12 hours × 30 days) increased Cmax and AUC of prednisolone (60 mg single dose) by an average of 11% and 34%, respectively, in healthy subjects [see Warnings and Precautions (5.8)].

Digoxin (P-glycoprotein mediated transport)–Voriconazole (200 mg every 12 hours × 12 days) had no significant effect on steady state Cmax and AUCτ of digoxin (0.25 mg once daily for 10 days) in healthy subjects.

Mycophenolic acid (UDP-glucuronyl transferase substrate)–Voriconazole (200 mg every 12 hours × 5 days) had no significant effect on the Cmax and AUCτ of mycophenolic acid and its major metabolite, mycophenolic acid glucuronide after administration of a 1 gram single oral dose of mycophenolate mofetil.

Two-Way Interactions

Concomitant use of the following agents with voriconazole is contraindicated:

Rifabutin (potent CYP450 inducer)–Rifabutin (300 mg once daily) decreased the Cmax and AUCτ of voriconazole at 200 mg twice daily by an average of 67% (90% CI: 58%, 73%) and 79% (90% CI: 71%, 84%), respectively, in healthy subjects. During coadministration with rifabutin (300 mg once daily), the steady state Cmax and AUCτ of voriconazole following an increased dose of 400 mg twice daily were on average approximately 2 times higher, compared with voriconazole alone at 200 mg twice daily. Coadministration of voriconazole at 400 mg twice daily with rifabutin 300 mg twice daily increased the Cmax and AUCτ of rifabutin by an average of 3-times (90% CI: 2.2, 4.0) and 4 times (90% CI: 3.5, 5.4), respectively, compared to rifabutin given alone [see Contraindications (4)].

Significant drug interactions that may require dosage adjustment, frequent monitoring of drug levels and/or frequent monitoring of drug-related adverse reactions/toxicity:

Efavirenz, a non-nucleoside reverse transcriptase inhibitor (CYP450 inducer; CYP3A4 inhibitor and substrate)–Standard doses of voriconazole and efavirenz (400 mg every 24 hours or higher) must not be coadministered [see Drug Interactions (7)]. Steady state efavirenz (400 mg PO every 24 hours) decreased the steady state Cmax and AUCτ of voriconazole (400 mg PO every 12 hours for 1 day, then 200 mg PO every 12 hours for 8 days) by an average of 61% and 77%, respectively, in healthy male subjects. Voriconazole at steady state (400 mg PO every 12 hours for 1 day, then 200 mg every 12 hours for 8 days) increased the steady state Cmax and AUCτ of efavirenz (400 mg PO every 24 hours for 9 days) by an average of 38% and 44%, respectively, in healthy subjects.

The pharmacokinetics of adjusted doses of voriconazole and efavirenz were studied in healthy male subjects following administration of voriconazole (400 mg PO every 12 hours on Days 2 to 7) with efavirenz (300 mg PO every 24 hours on Days 1–7), relative to steady state administration of voriconazole (400 mg for 1 day, then 200 mg PO every 12 hours for 2 days) or efavirenz (600 mg every 24 hours for 9 days). Coadministration of voriconazole 400 mg every 12 hours with efavirenz 300 mg every 24 hours, decreased voriconazole AUCτ by 7% (90% CI: -23%, 13%) and increased Cmax by 23% (90% CI: -1%, 53%); efavirenz AUCτ was increased by 17% (90% CI: 6%, 29%) and Cmax was equivalent [see Dosage and Administration (2.7), Contraindications (4), and Drug Interactions (7)].

Phenytoin (CYP2C9 substrate and potent CYP450 inducer)–Repeat dose administration of phenytoin (300 mg once daily) decreased the steady state Cmax and AUCτ of orally administered voriconazole (200 mg every 12 hours × 14 days) by an average of 50% and 70%, respectively, in healthy subjects. Administration of a higher voriconazole dose (400 mg every 12 hours × 7 days) with phenytoin (300 mg once daily) resulted in comparable steady state voriconazole Cmax and AUCτ estimates as compared to when voriconazole was given at 200 mg every 12 hours without phenytoin [see Dosage and Administration (2.7) and Drug Interactions (7)].

Repeat dose administration of voriconazole (400 mg every 12 hours × 10 days) increased the steady state Cmax and AUCτ of phenytoin (300 mg once daily) by an average of 70% and 80%, respectively, in healthy subjects. The increase in phenytoin Cmax and AUC when coadministered with voriconazole may be expected to be as high as 2 times the Cmax and AUC estimates when phenytoin is given without voriconazole [see Drug Interactions (7)].

Omeprazole (CYP2C19 inhibitor; CYP2C19 and CYP3A4 substrate)–Coadministration of omeprazole (40 mg once daily × 10 days) with oral voriconazole (400 mg every 12 hours × 1 day, then 200 mg every 12 hours × 9 days) increased the steady state Cmax and AUCτ of voriconazole by an average of 15% (90% CI: 5%, 25%) and 40% (90% CI: 29%, 55%), respectively, in healthy subjects. No dosage adjustment of voriconazole is recommended.

Coadministration of voriconazole (400 mg every 12 hours × 1 day, then 200 mg × 6 days) with omeprazole (40 mg once daily × 7 days) to healthy subjects significantly increased the steady state Cmax and AUCτ of omeprazole an average of 2 times (90% CI: 1.8, 2.6) and 4 times (90% CI: 3.3, 4.4), respectively, as compared to when omeprazole is given without voriconazole [see Drug Interactions (7)].

Oral Contraceptives (CYP3A4 substrate; CYP2C19 inhibitor)–Coadministration of oral voriconazole (400 mg every 12 hours for 1 day, then 200 mg every 12 hours for 3 days) and oral contraceptive (Ortho-Novum1/35® consisting of 35 mcg ethinyl estradiol and 1 mg norethindrone, every 24 hours) to healthy female subjects at steady state increased the Cmax and AUCτ of ethinyl estradiol by an average of 36% (90% CI: 28%, 45%) and 61% (90% CI: 50%, 72%), respectively, and that of norethindrone by 15% (90% CI: 3%, 28%) and 53% (90% CI: 44%, 63%), respectively in healthy subjects. Voriconazole Cmax and AUCτ increased by an average of 14% (90% CI: 3%, 27%) and 46% (90% CI: 32%, 61%), respectively [see Drug Interactions (7)].

No significant pharmacokinetic interaction was seen and no dosage adjustment of these drugs is recommended:

Indinavir (CYP3A4 inhibitor and substrate)–Repeat dose administration of indinavir (800 mg TID for 10 days) had no significant effect on voriconazole Cmax and AUC following repeat dose administration (200 mg every 12 hours for 17 days) in healthy subjects.

Repeat dose administration of voriconazole (200 mg every 12 hours for 7 days) did not have a significant effect on steady state Cmax and AUCτ of indinavir following repeat dose administration (800 mg TID for 7 days) in healthy subjects.

12.4 Microbiology

Mechanism of Action

Voriconazole is an azole antifungal drug. The primary mode of action of voriconazole is the inhibition of fungal cytochrome P-450-mediated 14 alpha-lanosterol demethylation, an essential step in fungal ergosterol biosynthesis. The accumulation of 14 alpha-methyl sterols correlates with the subsequent loss of ergosterol in the fungal cell wall and may be responsible for the antifungal activity of voriconazole.

Resistance

A potential for development of resistance to voriconazole is well known. The mechanisms of resistance may include mutations in the gene ERG11 (encodes for the target enzyme, lanosterol 14-α-demethylase), upregulation of genes encoding the ATP-binding cassette efflux transporters i.e., Candida drug resistance (CDR) pumps and reduced access of the drug to the target, or some combination of those mechanisms. The frequency of drug resistance development for the various fungi for which this drug is indicated is not known.

Fungal isolates exhibiting reduced susceptibility to fluconazole or itraconazole may also show reduced susceptibility to voriconazole, suggesting cross-resistance can occur among these azoles. The relevance of cross-resistance and clinical outcome has not been fully characterized. Clinical cases where azole cross-resistance is demonstrated may require alternative antifungal therapy.

Antimicrobial Activity

Voriconazole has been shown to be active against most isolates of the following microorganisms, both in vitro and in clinical infections.

Aspergillus fumigatus
Aspergillus flavus
Aspergillus niger
Aspergillus terreus
Candida albicans
Candida glabrata (In clinical studies, the voriconazole MIC90 was 4 µg/mL) [In clinical studies, voriconazole MIC90 for C. glabrata baseline isolates was 4 µg/mL; 13/50 (26%) C. glabrata baseline isolates were resistant (MIC ≥4 µg/mL) to voriconazole. However, based on 1054 isolates tested in surveillance studies the MIC90 was 1 µg/mL.]
Candida krusei
Candida parapsilosis
Candida tropicalis
Fusarium spp. including Fusarium solani
Scedosporium apiospermum

The following data are available, but their clinical significance is unknown. At least 90 percent of the following fungi exhibit an in vitro minimum inhibitory concentration (MIC) less than or equal to the susceptible breakpoint for voriconazole against isolates of similar genus or organism group. However, the effectiveness of voriconazole in treating clinical infections due to these fungi has not been established in adequate and well-controlled clinical trials:

Candida lusitaniae
Candida guilliermondii

Susceptibility Testing

For specific information regarding susceptibility test interpretive criteria and associated test methods and quality control standards recognized by FDA for this drug, please see: https://www.fda.gov/STIC.

12.5 Pharmacogenomics

CYP2C19, significantly involved in the metabolism of voriconazole, exhibits genetic polymorphism. Approximately 15–20% of Asian populations may be expected to be poor metabolizers. For Caucasians and Blacks, the prevalence of poor metabolizers is 3–5%. Studies conducted in Caucasian and Japanese healthy subjects have shown that poor metabolizers have, on average, 4-fold higher voriconazole exposure (AUCτ) than their homozygous extensive metabolizer counterparts. Subjects who are heterozygous extensive metabolizers have, on average, 2-fold higher voriconazole exposure than their homozygous extensive metabolizer counterparts [see Clinical Pharmacology (12.3)].

13 NONCLINICAL TOXICOLOGY

13.1 Carcinogenesis, Mutagenesis, Impairment of Fertility

Two-year carcinogenicity studies were conducted in rats and mice. Rats were given oral doses of 6, 18 or 50 mg/kg voriconazole, or 0.2, 0.6, or 1.6 times the RMD on a body surface area basis. Hepatocellular adenomas were detected in females at 50 mg/kg and hepatocellular carcinomas were found in males at 6 and 50 mg/kg. Mice were given oral doses of 10, 30 or 100 mg/kg voriconazole, or 0.1, 0.4, or 1.4 times the RMD on a body surface area basis. In mice, hepatocellular adenomas were detected in males and females and hepatocellular carcinomas were detected in males at 1.4 times the RMD of voriconazole.

Voriconazole demonstrated clastogenic activity (mostly chromosome breaks) in human lymphocyte cultures in vitro. Voriconazole was not genotoxic in the Ames assay, CHO HGPRT assay, the mouse micronucleus assay or the in vivo DNA repair test (Unscheduled DNA Synthesis assay).

Voriconazole administration induced no impairment of male or female fertility in rats dosed at 50 mg/kg, or 1.6 times the RMD.

14 CLINICAL STUDIES

Voriconazole, administered orally or parenterally, has been evaluated as primary or salvage therapy in 520 patients aged 12 years and older with infections caused by Aspergillus spp., Fusarium spp., and Scedosporium spp.

14.1 Invasive Aspergillosis (IA)

Voriconazole was studied in patients for primary therapy of IA (randomized, controlled study 307/602), for primary and salvage therapy of aspergillosis (non-comparative study 304) and for treatment of patients with IA who were refractory to, or intolerant of, other antifungal therapy (non-comparative study 309/604).

Study 307/602 – Primary Therapy of Invasive Aspergillosis

The efficacy of voriconazole compared to amphotericin B in the primary treatment of acute IA was demonstrated in 277 patients treated for 12 weeks in a randomized, controlled study (Study 307/602). The majority of study patients had underlying hematologic malignancies, including bone marrow transplantation. The study also included patients with solid organ transplantation, solid tumors, and AIDS. The patients were mainly treated for definite or probable IA of the lungs. Other aspergillosis infections included disseminated disease, CNS infections and sinus infections. Diagnosis of definite or probable IA was made according to criteria modified from those established by the National Institute of Allergy and Infectious Diseases Mycoses Study Group/European Organisation for Research and Treatment of Cancer (NIAID MSG/EORTC).

Voriconazole was administered intravenously with a loading dose of 6 mg/kg every 12 hours for the first 24 hours followed by a maintenance dose of 4 mg/kg every 12 hours for a minimum of 7 days. Therapy could then be switched to the oral formulation at a dose of 200 mg every 12 hours. Median duration of IV voriconazole therapy was 10 days (range 2–85 days). After IV voriconazole therapy, the median duration of PO voriconazole therapy was 76 days (range 2–232 days).

Patients in the comparator group received conventional amphotericin B as a slow infusion at a daily dose of 1.0–1.5 mg/kg/day. Median duration of IV amphotericin therapy was 12 days (range 1–85 days). Treatment was then continued with OLAT, including itraconazole and lipid amphotericin B formulations. Although initial therapy with conventional amphotericin B was to be continued for at least two weeks, actual duration of therapy was at the discretion of the investigator. Patients who discontinued initial randomized therapy due to toxicity or lack of efficacy were eligible to continue in the study with OLAT treatment.

A satisfactory global response at 12 weeks (complete or partial resolution of all attributable symptoms, signs, radiographic/bronchoscopic abnormalities present at baseline) was seen in 53% of voriconazole treated patients compared to 32% of amphotericin B treated patients (Table 15). A benefit of voriconazole compared to amphotericin B on patient survival at Day 84 was seen with a 71% survival rate on voriconazole compared to 58% on amphotericin B (Table 13).

Table 13 also summarizes the response (success) based on mycological confirmation and species.

Table 13: Overall Efficacy and Success by Species in the Primary Treatment of Acute Invasive Aspergillosis Study 307/602
 | Voriconazole | Ampho B [Amphotericin B followed by other licensed antifungal therapy] | Stratified Difference (95% CI) [Difference and corresponding 95% confidence interval are stratified by protocol]
 | n/N (%) | n/N (%)
Efficacy as Primary Therapy
Satisfactory Global Response [Assessed by independent Data Review Committee (DRC)] | 76/144 (53) | 42/133 (32) | 21.8% (10.5%, 33.0%) p<0.0001
Survival at Day 84 [Proportion of subjects alive] | 102/144 (71) | 77/133 (58) | 13.1% (2.1%, 24.2%)
Success by Species
 | Success n/N (%)
Overall success | 76/144 (53) | 42/133 (32)
Mycologically confirmed [Not all mycologically confirmed specimens were speciated] | 37/84 (44) | 16/67 (24)
Aspergillus spp. [Some patients had more than one species isolated at baseline]
A. fumigatus | 28/63 (44) | 12/47 (26)
A. flavus | 3/6 | 4/9
A. terreus | 2/3 | 0/3
A. niger | 1/4 | 0/9
A. nidulans | 1/1 | 0/0

Study 304 – Primary and Salvage Therapy of Aspergillosis

In this non-comparative study, an overall success rate of 52% (26/50) was seen in patients treated with voriconazole for primary therapy. Success was seen in 17/29 (59%) with Aspergillus fumigatus infections and 3/6 (50%) patients with infections due to non-fumigatus species [A. flavus (1/1); A. nidulans (0/2); A. niger (2/2); A. terreus (0/1)]. Success in patients who received voriconazole as salvage therapy is presented in Table 14.

Study 309/604 – Treatment of Patients with Invasive Aspergillosis who were Refractory to, or Intolerant of, other Antifungal Therapy

Additional data regarding response rates in patients who were refractory to, or intolerant of, other antifungal agents are also provided in Table 16. In this non-comparative study, overall mycological eradication for culture-documented infections due to fumigatus and non-fumigatus species of Aspergillus was 36/82 (44%) and 12/30 (40%), respectively, in voriconazole treated patients. Patients had various underlying diseases and species other than A. fumigatus contributed to mixed infections in some cases.

For patients who were infected with a single pathogen and were refractory to, or intolerant of, other antifungal agents, the satisfactory response rates for voriconazole in studies 304 and 309/604 are presented in Table 14.

Table 14: Combined Response Data in Salvage Patients with Single Aspergillus Species (Studies 304 and 309/604)
 | Success n/N
A. fumigatus | 43/97 (44%)
A. flavus | 5/12
A. nidulans | 1/3
A. niger | 4/5
A. terreus | 3/8
A. versicolor | 0/1

Nineteen patients had more than one species of Aspergillus isolated. Success was seen in 4/17 (24%) of these patients.

14.2 Candidemia in Non-neutropenic Patients and Other Deep Tissue Candida Infections

Voriconazole was compared to the regimen of amphotericin B followed by fluconazole in Study 608, an open-label, comparative study in nonneutropenic patients with candidemia associated with clinical signs of infection. Patients were randomized in 2:1 ratio to receive either voriconazole (n=283) or the regimen of amphotericin B followed by fluconazole (n=139). Patients were treated with randomized study drug for a median of 15 days. Most of the candidemia in patients evaluated for efficacy was caused by C. albicans (46%), followed by C. tropicalis (19%), C. parapsilosis (17%), C. glabrata (15%), and C. krusei (1%).

An independent Data Review Committee (DRC), blinded to study treatment, reviewed the clinical and mycological data from this study, and generated one assessment of response for each patient. A successful response required all of the following: resolution or improvement in all clinical signs and symptoms of infection, blood cultures negative for Candida, infected deep tissue sites negative for Candida or resolution of all local signs of infection, and no systemic antifungal therapy other than study drug. The primary analysis, which counted DRC-assessed successes at the fixed time point (12 weeks after End of Therapy [EOT]), demonstrated that voriconazole was comparable to the regimen of amphotericin B followed by fluconazole (response rates of 41% and 41%, respectively) in the treatment of candidemia. Patients who did not have a 12-week assessment for any reason were considered a treatment failure.

The overall clinical and mycological success rates by Candida species in Study 150-608 are presented in Table 15.

Table 15: Overall Success Rates Sustained From EOT To The Fixed 12-Week Follow-Up Time Point By Baseline Pathogen [A few patients had more than one pathogen at baseline.] , [Patients who did not have a 12-week assessment for any reason were considered a treatment failure.]
Baseline Pathogen | Clinical and Mycological Success (%)
Baseline Pathogen | Voriconazole | Amphotericin B --> Fluconazole
C. albicans | 46/107 (43%) | 30/63 (48%)
C. tropicalis | 17/53 (32%) | 1/16 (6%)
C. parapsilosis | 24/45 (53%) | 10/19 (53%)
C. glabrata | 12/36 (33%) | 7/21 (33%)
C. krusei | 1/4 | 0/1

In a secondary analysis, which counted DRC-assessed successes at any time point (EOT, or 2, 6, or 12 weeks after EOT), the response rates were 65% for voriconazole and 71% for the regimen of amphotericin B followed by fluconazole.

In Studies 608 and 309/604 (non-comparative study in patients with invasive fungal infections who were refractory to, or intolerant of, other antifungal agents), voriconazole was evaluated in 35 patients with deep tissue Candida infections. A favorable response was seen in 4 of 7 patients with intra-abdominal infections, 5 of 6 patients with kidney and bladder wall infections, 3 of 3 patients with deep tissue abscess or wound infection, 1 of 2 patients with pneumonia/pleural space infections, 2 of 4 patients with skin lesions, 1 of 1 patients with mixed intra-abdominal and pulmonary infection, 1 of 2 patients with suppurative phlebitis, 1 of 3 patients with hepatosplenic infection, 1 of 5 patients with osteomyelitis, 0 of 1 with liver infection, and 0 of 1 with cervical lymph node infection.

14.3 Esophageal Candidiasis (EC)

The efficacy of oral voriconazole 200 mg twice daily compared to oral fluconazole 200 mg once daily in the primary treatment of EC was demonstrated in Study 150-305, a double-blind, double-dummy study in immunocompromised patients with endoscopically-proven EC. Patients were treated for a median of 15 days (range 1 to 49 days). Outcome was assessed by repeat endoscopy at end of treatment (EOT). A successful response was defined as a normal endoscopy at EOT or at least a 1 grade improvement over baseline endoscopic score. For patients in the Intent-to-Treat (ITT) population with only a baseline endoscopy, a successful response was defined as symptomatic cure or improvement at EOT compared to baseline. Voriconazole and fluconazole (200 mg once daily) showed comparable efficacy rates against EC, as presented in Table 16.

Table 16: Success Rates in Patients Treated for Esophageal Candidiasis
Population | Voriconazole | Fluconazole | Difference % (95% CI) [Confidence Interval for the difference (Voriconazole – Fluconazole) in success rates.]
PP [PP (Per Protocol) patients had confirmation of Candida esophagitis by endoscopy, received at least 12 days of treatment, and had a repeat endoscopy at EOT (end of treatment).] | 113/115 (98.2%) | 134/141 (95.0%) | 3.2 (-1.1, 7.5)
ITT [ITT (Intent to Treat) patients without endoscopy or clinical assessment at EOT were treated as failures.] | 175/200 (87.5%) | 171/191 (89.5%) | -2.0 (-8.3, 4.3)

Microbiologic success rates by Candida species are presented in Table 17.

Table 17: Clinical and Mycological Outcome by Baseline Pathogen in Patients with Esophageal Candidiasis (Study-150-305)
Pathogen [Some patients had more than one species isolated at baseline.] | Voriconazole |  | Fluconazole
Pathogen [Some patients had more than one species isolated at baseline.] | Favorable endoscopic response [Patients with endoscopic and/or mycological assessment at end of therapy.] | Mycological eradication | Favorable endoscopic response | Mycological eradication
Pathogen [Some patients had more than one species isolated at baseline.] | Success/Total (%) | Eradication/Total (%) | Success/Total (%) | Eradication/Total (%)
C. albicans | 134/140 (96%) | 90/107 (84%) | 147/156 (94%) | 91/115 (79%)
C. glabrata | 8/8 (100%) | 4/7 (57%) | 4/4 (100%) | 1/4 (25%)
C. krusei | 1/1 | 1/1 | 2/2 (100%) | 0/0

14.4 Other Serious Fungal Pathogens

In pooled analyses of patients, voriconazole was shown to be effective against the following additional fungal pathogens:

Scedosporium apiospermum - Successful response to voriconazole therapy was seen in 15 of 24 patients (63%). Three of these patients relapsed within 4 weeks, including 1 patient with pulmonary, skin and eye infections, 1 patient with cerebral disease, and 1 patient with skin infection. Ten patients had evidence of cerebral disease and 6 of these had a successful outcome (1 relapse). In addition, a successful response was seen in 1 of 3 patients with mixed organism infections.

Fusarium spp. - Nine of 21 (43%) patients were successfully treated with voriconazole. Of these 9 patients, 3 had eye infections, 1 had an eye and blood infection, 1 had a skin infection, 1 had a blood infection alone, 2 had sinus infections, and 1 had disseminated infection (pulmonary, skin, hepatosplenic). Three of these patients (1 with disseminated disease, 1 with an eye infection and 1 with a blood infection) had Fusarium solani and were complete successes. Two of these patients relapsed, 1 with a sinus infection and profound neutropenia and 1 post surgical patient with blood and eye infections.

14.5 Pediatric Studies

A total of 22 patients aged 12 to 18 years with IA were included in the adult therapeutic studies. Twelve out of 22 (55%) patients had successful response after treatment with a maintenance dose of voriconazole 4 mg/kg every 12 hours.

Fifty-three pediatric patients aged 2 to less than 18 years old were treated with voriconazole in two prospective, open-label, non-comparative, multicenter clinical studies.

One study was designed to enroll pediatric patients with IA or infections with rare molds (such as Scedosporium or Fusarium). Patients aged 2 to less than 12 years and 12 to 14 years with body weight less than 50 kg received an intravenous VFEND loading dose of 9 mg/kg every 12 hours for the first 24-hours followed by an 8 mg/kg intravenous maintenance dose every 12 hours. After completing 7 days of intravenous therapy patients had an option to switch to oral VFEND. The oral maintenance dose was 9 mg/kg every 12 hours (maximum dose of 350 mg). All other pediatric patients aged 12 to less than 18 years received the adult VFEND dosage regimen. Patients received VFEND for at least 6 weeks and up to a maximum of 12 weeks.

The study enrolled 31 patients with possible, proven, or probable IA. Fourteen of 31 patients, 5 of whom were 2 to less than 12 years old and 9 of whom were 12 to less than 18 years old, had proven or probable IA and were included in the modified intent-to-treat (MITT) efficacy analyses. No patients with rare mold were enrolled. A successful global response was defined as resolution or improvement in clinical signs and symptoms and at least 50% resolution of radiological lesions attributed to IA. The overall rate of successful global response at 6 weeks in the MITT population is presented in Table 18 below.

Table 18: Global Response [Global response rate was defined as the number of subjects with a successful response (complete or partial) as a percentage of all subjects (including subjects with an indeterminate or missing response) at 6 weeks in the MITT population.] in Patients with Invasive Aspergillosis, Modified Intent-to-Treat (MITT) [The Modified Intent-to-Treat (MITT) population was defined as all subjects who received at least 1 dose of study drug and who were diagnosed with proven or probable IA as defined by the modified EORTC/MSG criteria.] Population
Parameter | Global Response at Week 6
Parameter | Ages 2–<12 years N=5 | Ages 12–<18 years N=9 | Overall N=14
Number of successes, n (%) | 2 (40%) | 7 (78%) | 9 (64%)

The second study enrolled 22 patients with invasive candidiasis including candidemia (ICC) and EC requiring either primary or salvage therapy. Patients with ICC aged 2 to less than 12 years and 12 to 14 years with body weight less than 50 kg received an intravenous VFEND loading dose of 9 mg/kg every 12 hours for the first 24 hours followed by an 8 mg/kg intravenous maintenance dose every 12-hours. After completing 5 days of intravenous therapy patients had an option to switch to oral VFEND. The oral maintenance dose was 9 mg/kg every 12 hours (maximum dose of 350 mg). All other pediatric patients aged 12 to less than 18 years received the adult VFEND dosage regimen. VFEND was administered for at least 14 days after the last positive culture. A maximum of 42 days of treatment was permitted.

Patients with primary or salvage EC aged 2 to less than 12 years and 12 to 14 years with body weight less than 50 kg received an intravenous VFEND dose of 4 mg/kg every 12 hours followed by an oral VFEND dose of 9 mg/kg every 12 hours (maximum dose of 350 mg) when criteria for oral switch were met. All other pediatric patients aged 12 to less than 18 years received the adult VFEND dosage regimen. VFEND was administered for at least 7 days after the resolution of clinical signs and symptoms. A maximum of 42 days of treatment was permitted.

For EC, study treatment was initiated without a loading dose of intravenous voriconazole. Seventeen of these patients had confirmed Candida infection and were included in the MITT efficacy analyses. Of the 17 patients included in the MITT analyses, 9 were 2 to less than 12 years old (7 with ICC and 2 with EC) and 8 were 12 to less than 18 years old (all with EC). For ICC and EC, a successful global response was defined as clinical cure or improvement with microbiological eradication or presumed eradication. The overall rate of successful global response at EOT in the MITT population is presented in Table 19 below.

Table 19: Global Response [Global response was determined based on the investigator's assessment of clinical and microbiological response in the Modified Intent-to-Treat (MITT) analysis population at end of treatment. Subjects with missing data or whose response was deemed indeterminate were considered failures.] at the End of Treatment in the Treatment of Invasive Candidiasis with Candidemia and Esophageal Candidiasis Modified Intent-to-Treat (MITT) Population [The MITT population was defined as all subjects who received at least 1 dose of study drug and who had microbiologically confirmed invasive candidiasis with candidemia (ICC) and EC, or subjects with EC who had at least confirmation of oropharyngeal candidiasis without confirmation on esophagoscopy.]
Parameter | Global Response at End of Treatment
Parameter | EC N=10 |  |  | ICC [All subjects with ICC were aged 2 to less than 12.] N=7
Parameter | Ages 2–<12 N=2 | Ages 12–<18 N=8 | Overall N=10 | Overall N=7
Number of successes, n (%) | 2 (100%) | 5 (63%) | 7 (70%) | 6 (86%)

16 HOW SUPPLIED/STORAGE AND HANDLING

16.1 How Supplied

Powder for Solution for Injection

VFEND I.V. for Injection is supplied in a single-dose vial as a sterile lyophilized powder equivalent to 200 mg voriconazole and 3,200 mg sulfobutyl ether beta-cyclodextrin sodium (SBECD). It does not contain preservatives and is not made with natural rubber latex.

Individually packaged vials of 200 mg VFEND I.V.

(NDC 0049-3190-28)

Tablets

VFEND 50 mg tablets; white, film-coated, round, debossed with "Pfizer" on one side and "VOR50" on the reverse.

Bottles of 30 (NDC 0049-3170-30)

VFEND 200 mg tablets; white, film-coated, capsule shaped, debossed with "Pfizer" on one side and "VOR200" on the reverse.

Bottles of 30 (NDC 0049-3180-30)

Powder for Oral Suspension

VFEND for Oral Suspension is supplied in 100 mL high density polyethylene (HDPE) bottles. Each bottle contains 45 grams of powder for oral suspension, which contain 3 g of voriconazole. Following reconstitution, the volume of the suspension is 75 mL, providing a usable volume of 70 mL. Each mL of the oral suspension contains 40 mg of voriconazole (200 mg of voriconazole per 5 mL). A 5 mL oral dispenser and a press-in bottle adaptor are also provided.

(NDC 0049-3160-44)

16.2 Storage

VFEND I.V. for Injection unreconstituted vials should be stored at 15°C to 30°C (59°F to 86°F) [see USP Controlled Room Temperature]. VFEND is a single dose unpreserved sterile lyophile. From a microbiological point of view, following reconstitution of the lyophile with Water for Injection, the reconstituted solution should be used immediately. If not used immediately, in-use storage times and conditions prior to use are the responsibility of the user and should not be longer than 24 hours at 2°C to 8°C (36°F to 46°F). Chemical and physical in-use stability has been demonstrated for 24 hours at 2°C to 8°C (36°F to 46°F). This medicinal product is for single use only and any unused solution should be discarded. Only clear solutions without particles should be used [see Dosage and Administration (2.1)].

VFEND Tablets should be stored at 15°C to 30°C (59°F to 86°F) [see USP Controlled Room Temperature].

VFEND Powder for Oral Suspension should be stored at 2°C to 8°C (36°F to 46° F) (in a refrigerator) before reconstitution. The shelf-life of the powder for oral suspension is 24 months.

The reconstituted suspension should be stored at 15°C to 30°C (59°F to 86°F) [see USP Controlled Room Temperature]. Do not refrigerate or freeze. Keep the container tightly closed. The shelf-life of the reconstituted suspension is 14 days. Any remaining suspension should be discarded 14 days after reconstitution.

17 PATIENT COUNSELING INFORMATION

Advise the patient to read the FDA-approved patient labeling (Patient Information).

Visual Disturbances

Patients should be instructed that visual disturbances such as blurring and sensitivity to light may occur with the use of VFEND.

Photosensitivity

- Advise patients of the risk of photosensitivity (with or without concomitant methotrexate), accelerated photoaging, and skin cancer.
- Advise patients that VFEND can cause serious photosensitivity and to immediately contact their healthcare provider for new or worsening skin rash.
- Advise patients to avoid exposure to direct sun light and to use measures such as protective clothing and sunscreen with high sun protection factor (SPF).

Embryo-Fetal Toxicity

- Advise female patients of the potential risks to a fetus.
- Advise females of reproductive potential to use effective contraception during treatment with VFEND.

This product's labeling may have been updated. For the most recent prescribing information, please visit www.pfizer.com.

LAB-0271-49.0

PATIENT INFORMATION
VFEND®
(VEE-fend)
(voriconazole)
tablets, for oral use
VFEND®
(VEE-fend)
(voriconazole)
for oral suspension
VFEND®
(VEE-fend)
(voriconazole)
for injection, for intravenous use

Read the Patient Information that comes with VFEND before you start taking it and each time you get a refill. There may be new information. This information does not take the place of talking with your healthcare provider about your condition or treatment.

What is VFEND?
VFEND is a prescription medicine used to treat certain serious fungal infections in your blood and body. These infections are called "aspergillosis," "esophageal candidiasis," "Scedosporium," "Fusarium," and "candidemia".

It is not known if VFEND is safe and effective in children younger than 2 years old.

Do not take VFEND if you:

- are allergic to voriconazole or any of the ingredients in VFEND. See the end of this leaflet for a complete list of ingredients in VFEND.
- are taking any of the following medicines:

- carbamazepine
- efavirenz
- eplerenone
- ergotamine, dihydroergotamine (ergot alkaloids)
- finerenone
- ivabradine
- long-acting barbiturates like phenobarbital

- lurasidone
- naloxegol
- pimozide
- quinidine
- rifabutin
- rifampin
- ritonavir

- sirolimus
- St. John’s Wort (herbal supplement)
- tolvaptan
- venetoclax
- voclosporin

Ask your healthcare provider or pharmacist if you are not sure if you are taking any of the medicines listed above.
Do not start taking a new medicine without talking to your healthcare provider or pharmacist.

Before you take VFEND, tell your healthcare provider about all of your medical conditions, including if you:

- have or ever had heart disease, or an abnormal heart rate or rhythm. Your healthcare provider may order a test to check your heart (EKG) before starting VFEND.
- have low potassium levels, low magnesium levels, and low calcium levels. Your healthcare provider may do blood tests before starting and during treatment with VFEND.
- have liver or kidney problems. Your healthcare provider may do blood tests to make sure you can take VFEND.
- have trouble digesting dairy products, lactose (milk sugar), or regular table sugar. VFEND tablets contain lactose. VFEND oral suspension contains sucrose (table sugar).
- are pregnant or plan to become pregnant. VFEND can harm your unborn baby. Talk to your healthcare provider if you are pregnant or plan to become pregnant. Women who can become pregnant should use effective birth control while taking VFEND. Talk to your healthcare provider about birth control methods that may be right for you.
- are breastfeeding or plan to breastfeed. It is not known if VFEND passes into breast milk. Talk to your healthcare provider about the best way to feed your baby if you take VFEND.

Tell your healthcare provider about all the medicines you take, including prescription and over-the-counter medicines, vitamins and herbal supplements.
VFEND may affect the way other medicines work, and other medicines may affect how VFEND works.
Know what medicines you take. Keep a list of them to show your healthcare provider or pharmacist when you get a new medicine.

How should I take VFEND?

- VFEND may be prescribed to you as:
  - VFEND I.V. (intravenous infusion) or
  - VFEND tablets or
  - VFEND oral suspension
- VFEND I.V. will be given to you by a healthcare provider over 1 to 3 hours.
- Take VFEND tablets or oral suspension exactly as your healthcare provider tells you to.
- Take VFEND tablets or oral suspension at least 1 hour before or at least 1 hour after meals.
- VFEND oral suspension will be mixed for you by your pharmacist. Shake the bottle of VFEND oral suspension for 10 seconds each time before you use it.
- Only use the oral dispenser that comes with your VFEND oral suspension to administer your medicine.
- Do not mix VFEND oral suspension with any other medicine, flavored liquid, or syrup.
- If you take too much VFEND, call your healthcare provider or go to the nearest hospital emergency room.

What should I avoid while taking VFEND?

- You should not drive at night while taking VFEND. VFEND can cause changes in your vision such as blurring or sensitivity to light.
- Do not drive or operate machinery, or do other dangerous activities until you know how VFEND affects you.
- Avoid direct sunlight. VFEND can make your skin sensitive to the sun and the light from sunlamps and tanning beds. You could get a severe sunburn. Use sunscreen and wear a hat and clothes that cover your skin if you have to be in sunlight. Talk to your healthcare provider if you get sunburn.

What are the possible side effects of VFEND?

VFEND may cause serious side effects including:

- liver problems. Symptoms of liver problems may include:

- itchy skin
- flu-like symptoms

- yellowing of your eyes
- nausea or vomiting

- feeling very tired

- serious heart problems. VFEND may cause changes in your heart rate or rhythm, including your heart stopping (cardiac arrest).
- allergic reactions. Symptoms of an allergic reaction may include:

- fever
- chest tightness
- nausea
- flushing

- sweating
- trouble breathing
- itching

- feels like your heart is beating fast (tachycardia)
- feel faint
- skin rash

- vision changes. Symptoms of vision changes may include:
  - blurred vision
  - changes in the way you see colors
- serious skin reactions. Symptoms of serious skin reactions may include:
  - rash or hives
  - mouth sores
  - blistering or peeling of your skin
  - trouble swallowing or breathing
- sensitivity to light or sun (photosensitivity). VFEND can cause serious photosensitivity. There is an increased chance of skin toxicity while taking VFEND. This can happen with or without taking other medicines like methotrexate. Photosensitivity reactions may also increase your risk of:
  - faster skin aging from the sun
  - skin cancer

Call your healthcare provider right away if you get a new skin rash or your skin rash gets worse.

- kidney problems. VFEND may cause new or worse problems with kidney function, including kidney failure. Your healthcare provider should check your kidney function while you are taking VFEND. Your healthcare provider will decide if you can keep taking VFEND.
- adrenal gland problems:
  - VFEND may cause reduced adrenal function (adrenal insufficiency).
  - VFEND may cause overactive adrenal function (Cushing’s syndrome) when voriconazole is used at the same time with corticosteroids.
Symptoms of adrenal insufficiency include:

- feeling tired
- nausea and vomiting
- abdominal pain

- lack of energy
- feeling dizzy or lightheaded

- weakness
- weight loss

Symptoms of Cushing's syndrome include:

- weight gain
- thinning skin
- excessive hair growth

- fatty hump between the shoulders (buffalo hump) and a rounded face (moon face)
- bruising easily
- excessive sweating

- darkening of the skin on the stomach, thighs, breasts, and arms
- high blood sugar

- inflammation of the pancreas (pancreatitis). Symptoms of pancreatitis may include pain in your stomach area (abdomen) that is severe and will not go away. The pain may be felt going from your abdomen to your back. The pain may happen with or without vomiting.
- bone problems. VFEND may cause weakening of bones and bone pain. Tell your healthcare provider if you have bone pain.

Call your healthcare provider or go to the nearest hospital emergency room right away if you have any of the symptoms listed above.

The most common side effects of VFEND in adults include:

- vision changes
- nausea
- hallucinations (seeing or hearing things that are not there)

- rash
- headache
- abnormal liver function tests
- chills

- vomiting
- fast heart beat (tachycardia)
- fever

The most common side effects of VFEND in children include:

- fever
- diarrhea
- low platelet counts
- abnormal liver function tests
- low blood calcium levels
- low blood phosphate levels
- vision changes
- rash
- stomach pain
- trouble breathing
- dizziness

- high blood pressure
- cough
- low blood pressure
- swelling in the arms and legs
- high blood sugar levels
- headache
- fast heart beat (tachycardia)
- nose bleeds
- low blood potassium levels
- low blood levels of albumin
- kidney problems

- inflammation of mucous membranes
- hallucinations (seeing or hearing things that are not there)
- coughing up blood
- constipation
- low blood magnesium levels
- fullness of the stomach area
- vomiting
- nausea
- upper respiratory tract infection

Tell your healthcare provider if you have any side effect that bothers you or that does not go away.
These are not all the possible side effects of VFEND.
Call your doctor for medical advice about side effects. You may report side effects to FDA at 1-800-FDA-1088.

How should I store VFEND?

- Store VFEND tablets and oral suspension at room temperature between 59°F to 86°F (15°C to 30°C). Do not refrigerate or freeze.
- VFEND oral suspension should be thrown away (discarded) after 14 days.
- Keep VFEND tablets and oral suspension in a tightly closed container.
- Safely throw away medicine that is out of date or no longer needed.
- Keep VFEND, as well as all other medicines, out of the reach of children.

General information about the safe and effective use of VFEND.
Medicines are sometimes prescribed for purposes other than those listed in a Patient Information leaflet. Do not use VFEND for a condition for which it was not prescribed. Do not give VFEND to other people, even if they have the same symptoms that you have. It may harm them.
You can ask your healthcare provider or pharmacist for information about VFEND that is written for health professionals.

What are the ingredients in VFEND?
Active ingredient: voriconazole.
Inactive ingredients:
VFEND IV: sulfobutyl ether beta-cyclodextrin sodium.
VFEND tablets: croscarmellose sodium, lactose monohydrate, magnesium stearate, povidone, pregelatinized starch, and a coating containing hypromellose, lactose monohydrate, titanium dioxide, and triacetin.
VFEND oral suspension: anhydrous citric acid, colloidal silicon dioxide, natural orange flavor, sodium benzoate, sodium citrate dihydrate, sucrose, titanium dioxide, and xanthan gum.

This product's labeling may have been updated. For the most recent prescribing information, please visit www.pfizer.com.
For more information, go to www.pfizer.com or call 1-800-438-1985.

This Patient Information has been approved by the U.S. Food and Drug Administration. Revised: 1/2026

LAB-0311-23.0

INSTRUCTIONS FOR USE VFEND® (VEE-fend) (voriconazole) for oral suspension

Read this Instructions for Use before you start taking VFEND and each time you get a refill. There may be new information. This information does not take the place of talking with your healthcare provider about your medical condition or treatment.

Important information:

- Follow your healthcare provider's instructions for the dose of VFEND to take.
- Ask your healthcare provider or pharmacist if you are not sure how to take VFEND.
- VFEND for oral suspension is a liquid form of VFEND. Your pharmacist will mix (reconstitute) the medicine before it is dispensed to you. If VFEND is still in powder form, do not use it. Return it to your pharmacist.
- Always use the oral dispenser provided with VFEND to make sure you measure the right amount of VFEND.
- Shake the closed bottle of mixed (reconstituted) oral suspension well for about 10 seconds before each use.

Each pack contains:

How to prepare the bottle and take VFEND:

1. | Remove the child-resistant bottle cap by pushing down while twisting the cap to the left (counter-clockwise). | 2. | Push the bottle adapter firmly into the bottle (if your pharmacist has not already inserted the bottle adapter). If the bottle adapter is missing, contact your pharmacist. Do not remove the bottle adapter after it is inserted. | 3. | Important: Bottle adapter must be fully inserted before use.
4. | The oral dispenser has markings to measure a dose that is a whole number (1 mL, 2 mL, 3 mL, 4 mL, or 5 mL) on one side and markings to measure a dose that is not a whole number (1.25 mL, 2.5 mL, or 3.75 mL) on the other side. Pull back on the oral dispenser blue plunger to your prescribed dose to fill the syringe with air. The picture below shows an example of a 3 mL dose. | 5. | Insert the tip of the oral dispenser into the bottle adapter. | 6. | While holding the bottle with 1 hand, push down on the oral dispenser blue plunger with your other hand to push air into the bottle.
7. | Turn the bottle upside down and slowly pull back on the oral dispenser blue plunger to withdraw your prescribed dose of medicine. | 8. | Turn the bottle back upright with the oral dispenser still in place. Remove the tip of the oral dispenser from the bottle adapter. Place the tip of the oral dispenser in your mouth and point the tip of the oral dispenser towards the inside of the cheek. Slowly push the plunger until all the medicine is given. Do not squirt the medicine out quickly. This may cause you to choke. If the medicine is to be given to a child, keep your child in an upright position while giving the medicine. If your dose is more than 5 mL, repeat step 4 through step 8 to give the remaining part of your dose. For example, if your dose is 8.75 mL measure and give 5 mL first and then measure and give 3.75 mL. | 9. | Screw the bottle cap back on the bottle tightly by turning the cap to the right (clockwise). Do not remove the bottle adapter. The bottle cap will fit over it.

Rinse the oral dispenser after each use.

- Pull the plunger out of the oral dispenser and wash both parts with warm soapy water.
- Rinse both parts with water and allow to air dry after each use.
- After air drying, push the plunger back into the oral dispenser.
- Store the oral dispenser with VFEND oral suspension in a clean safe place.

How should I store VFEND oral suspension?

- Store VFEND oral suspension at room temperature between 59°F to 86°F (15°C to 30°C).
- Do not refrigerate or freeze.
- Keep the bottle cap tightly closed.
- Use VFEND oral suspension within 14 days after it has been mixed (reconstituted) by the pharmacist. The pharmacist will write the expiration date on the bottle label (the expiration date of the oral suspension is 14 days from the date it was mixed (reconstituted) by the pharmacist). Throw away (discard) any unused VFEND after the expiration date.
- Keep VFEND and all medicines out of the reach of children.

This product's labeling may have been updated. For the most recent prescribing information, please visit www.pfizer.com.

This Instructions for Use has been approved by the U.S. Food and Drug Administration.

LAB-1348-6.0
Revised: 8/2024

PRINCIPAL DISPLAY PANEL - 50 mg Tablet Bottle Label

Pfizer

NDC 0049-3170-30

Vfend®
(voriconazole)

50 mg

Tablets

30 Tablets
Rx only

PRINCIPAL DISPLAY PANEL - 200 mg Tablet Bottle Label

Pfizer

NDC 0049-3180-30

Vfend®
(voriconazole)

200 mg

Tablets

30 Tablets
Rx only

PRINCIPAL DISPLAY PANEL - 200 mg Vial Label

NDC 0049-3190-28

Vfend® I.V.
(voriconazole) for injection
200 mg*
200 mg* of voriconazole

Not made with natural rubber latex
No Preservatives

Sterile Single-Dose Vial - Discard
Unused Portion
For Intravenous Infusion Only

Pfizer
Hospital

Rx only

PRINCIPAL DISPLAY PANEL - 200 mg Vial Carton

NDC 0049-3190-28
Rx only

1 Vial
Vfend® I.V.
(voriconazole) for injection

200 mg*
200 mg* of voriconazole

Not made with natural
rubber latex
No Preservatives

Sterile Single-Dose Vial -
Discard Unused Portion

For Intravenous Infusion Only

Pfizer
Hospital

PRINCIPAL DISPLAY PANEL - 40 mg Bottle Label

Pfizer
NDC 0049-3160-44

Vfend®
(voriconazole)
for oral suspension

40 mg/mL*

ORANGE FLAVORED

75 mL (when reconstituted)

Rx only

PRINCIPAL DISPLAY PANEL - 40 mg Bottle Carton

Pfizer
NDC 0049-3160-44

Vfend®
(voriconazole)
for oral suspension
40 mg/mL*

ORANGE FLAVORED

Oral Dispenser Included

Important: Read assembly instructions
carefully before dispensing.
Contains Small Parts -
Keep out of reach of children.

75 mL (when reconstituted)

Rx only